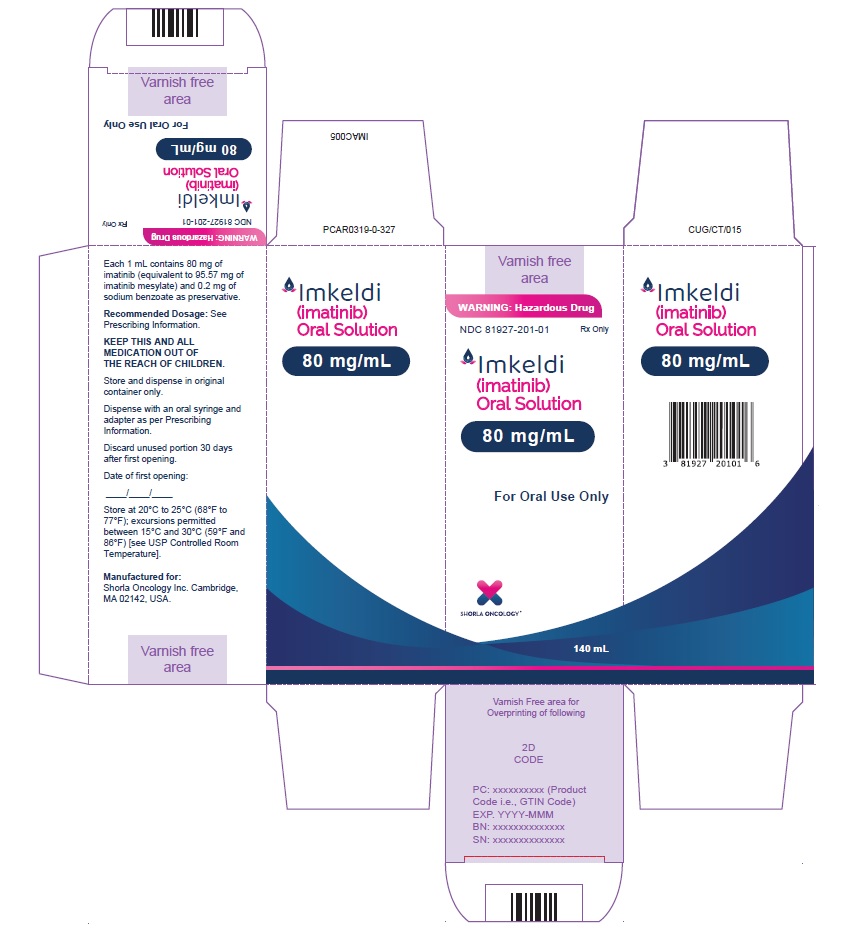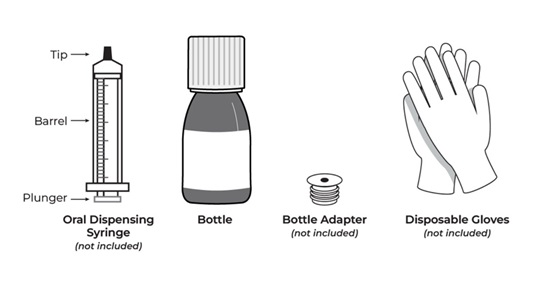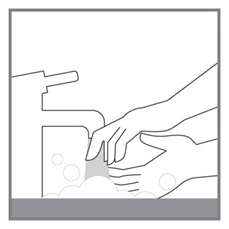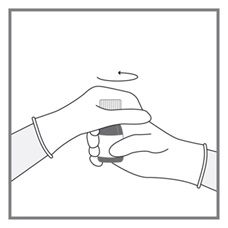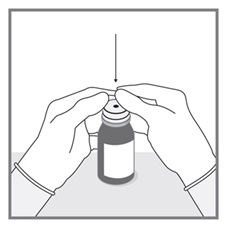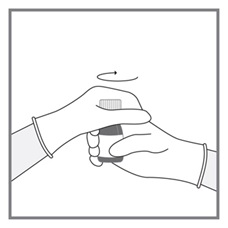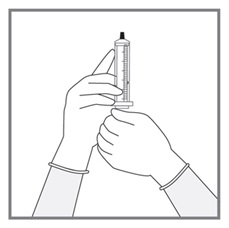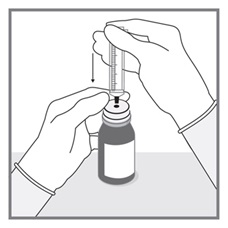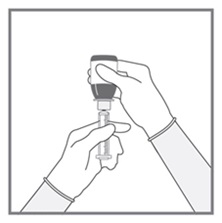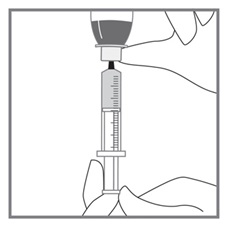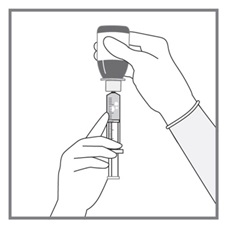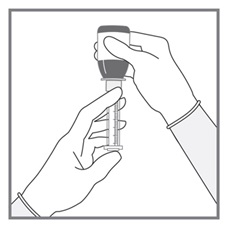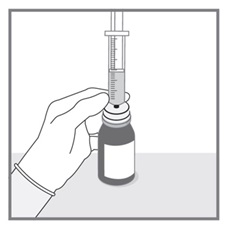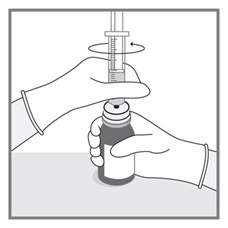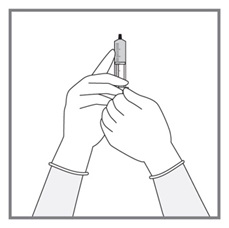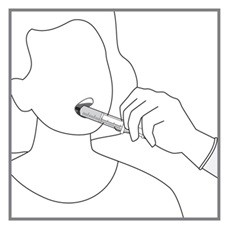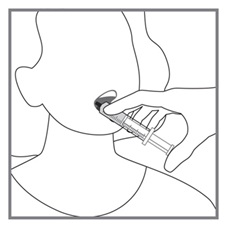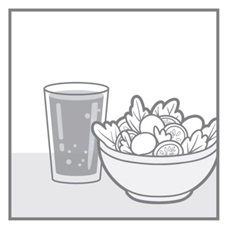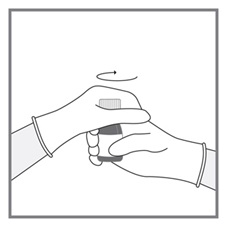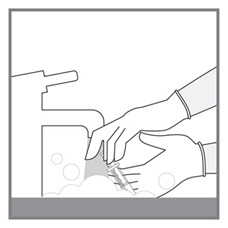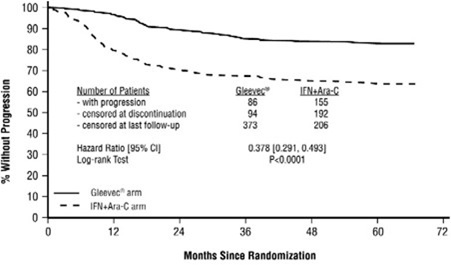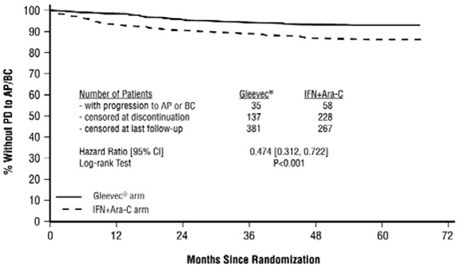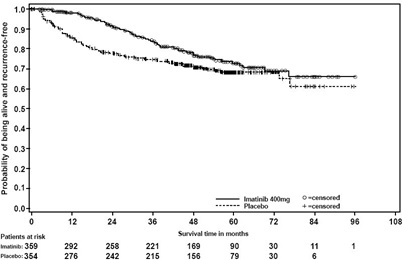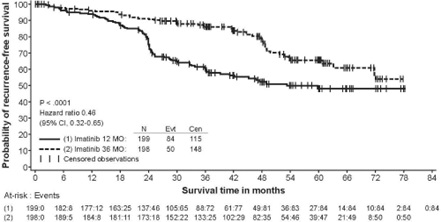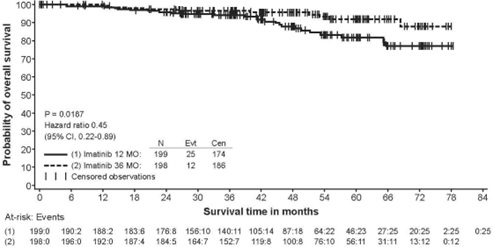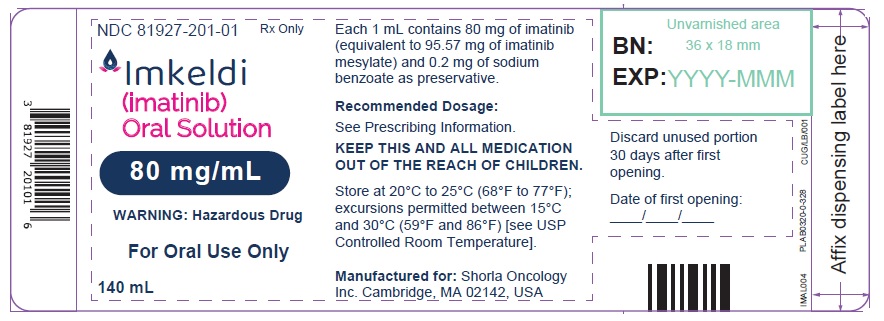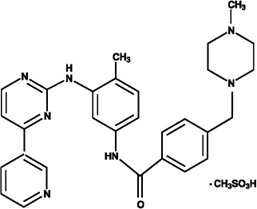 DRUG LABEL: IMKELDI
NDC: 81927-201 | Form: SOLUTION
Manufacturer: Shorla Oncology Inc.,
Category: prescription | Type: HUMAN PRESCRIPTION DRUG LABEL
Date: 20241205

ACTIVE INGREDIENTS: IMATINIB MESYLATE 80 mg/1 mL
INACTIVE INGREDIENTS: MALTITOL; GLYCERIN; SODIUM BENZOATE; ACESULFAME POTASSIUM; CITRIC ACID MONOHYDRATE; LACTIC ACID; TRIACETIN; WATER

HIGHLIGHTS OF PRESCRIBING INFORMATION

These highlights do not include all the information needed to use IMKELDI safely and effectively. See full prescribing information for IMKELDI.
IMKELDI (imatinib) oral solution
Initial U.S. Approval: 2001

1 INDICATIONS AND USAGE

Imkeldi is a kinase inhibitor indicated for the treatment of:

- Newly diagnosed adult and pediatric patients with Philadelphia chromosome positive chronic myeloid leukemia (Ph+ CML) in chronic phase. (1.1)
- Patients with Philadelphia chromosome positive chronic myeloid leukemia (Ph+ CML) in blast crisis (BC), accelerated phase (AP), or in chronic phase (CP) after failure of interferon-alpha therapy. (1.2)
- Adult patients with relapsed or refractory Philadelphia chromosome positive acute lymphoblastic leukemia (Ph+ ALL). (1.3)
- Pediatric patients with newly diagnosed Philadelphia chromosome positive acute lymphoblastic leukemia (Ph+ ALL) in combination with chemotherapy. (1.4)
- Adult patients with myelodysplastic/myeloproliferative diseases (MDS/MPD) associated with platelet-derived growth factor receptor (PDGFR) gene re-arrangements. (1.5)
- Adult patients with aggressive systemic mastocytosis (ASM) without the D816V c-Kit mutation or with c-Kit mutational status unknown. (1.6)
- Adult patients with hypereosinophilic syndrome (HES) and/or chronic eosinophilic leukemia (CEL) who have the FIP1L1-PDGFRα fusion kinase (mutational analysis or fluorescence in situ hybridization [FISH] demonstration of CHIC2 allele deletion) and for patients with HES and/or CEL who are FIP1L1-PDGFRα fusion kinase negative or unknown. (1.7)
- Adult patients with unresectable, recurrent and/or metastatic dermatofibrosarcoma protuberans (DFSP). (1.8)
- Patients with Kit (CD117) positive unresectable and/or metastatic malignant gastrointestinal stromal tumors (GIST). (1.9)
- Adjuvant treatment of adult patients following resection of Kit (CD117) positive GIST. (1.10)

2 DOSAGE AND ADMINISTRATION

- Adults with Ph+ CML CP (2.2): 400 mg/day
- Adults with Ph+ CML AP or BC (2.2): 600 mg/day
- Pediatrics with Ph+ CML CP (2.3): 340 mg/m^2/day
- Adults with Ph+ ALL (2.4): 600 mg/day
- Pediatrics with Ph+ ALL (2.5): 340 mg/m^2/day
- Adults with MDS/MPD (2.6): 400 mg/day
- Adults with ASM (2.7): 100 mg/day or 400 mg/day
- Adults with HES/CEL (2.8): 100 mg/day or 400 mg/day
- Adults with DFSP (2.9): 800 mg/day
- Adults with metastatic and/or unresectable GIST (2.10): 400 mg/day
- Adjuvant treatment of adults with GIST (2.11): 400 mg/day
- Patients with mild to moderate hepatic impairment (2.12): 400 mg/day
- Patients with severe hepatic impairment (2.12): 300 mg/day

All doses of Imkeldi should be taken with a meal and a large glass of water. Doses of 400 mg or 600 mg should be administered once daily, whereas a dose of 800 mg should be administered as 400 mg twice a day. Imkeldi is intended for oral use only. It is important that Imkeldi be measured with an accurate measuring device. A household teaspoon is not an accurate measuring device. A pharmacist can provide an appropriate press-in bottle adapter and oral dispensing syringe and can provide instructions for measuring the correct dose. (2.1, 5.15)

3 DOSAGE FORMS AND STRENGTHS

Oral solution: 80 mg/mL of imatinib (3)

4 CONTRAINDICATIONS

None. (4)

5 WARNINGS AND PRECAUTIONS

- Fluid Retention and Edema: Edema and severe fluid retention have occurred. Weigh patients regularly and manage unexpected rapid weight gain by drug interruption and diuretics. (5.1, 6.1)
- Hematologic Toxicity: Cytopenias, particularly anemia, neutropenia, and thrombocytopenia, have occurred. Manage with dose reduction, dose interruption, or discontinuation of treatment. Perform complete blood counts weekly for the first month, biweekly for the second month, and periodically thereafter. (5.2)
- Congestive Heart Failure and Left Ventricular Dysfunction: Severe congestive heart failure and left ventricular dysfunction have been reported, particularly in patients with comorbidities and risk factors. Monitor and treat patients with cardiac disease or risk factors for cardiac failure. (5.3)
- Hepatotoxicity: Severe hepatotoxicity, including fatalities may occur. Assess liver function before initiation of treatment and monthly thereafter or as clinically indicated. Monitor liver function when combined with chemotherapy known to be associated with liver dysfunction. (5.4)
- Hemorrhage: Grade 3/4 hemorrhage has been reported in clinical studies in patients with newly diagnosed CML and with GIST. GI tumor sites may be the source of GI bleeds in GIST. (5.5)
- Gastrointestinal Disorders: Gastrointestinal (GI) perforations, some fatal, have been reported. (5.6)
- Hypereosinophilic Cardiac Toxicity: Cardiogenic shock/left ventricular dysfunction has been associated with the initiation of Imkeldi in patients with conditions associated with high eosinophil levels (e.g., HES, MDS/MPD, and ASM). (5.7)
- Dermatologic Toxicities: Bullous dermatologic reactions (e.g., erythema multiforme and Stevens-Johnson syndrome) have been reported with the use of Imkeldi. (5.8)
- Hypothyroidism: Hypothyroidism has been reported in thyroidectomy patients undergoing levothyroxine replacement. Closely monitor TSH levels in such patients. (5.9)
- Embryo-Fetal Toxicity: Can cause fetal harm. Advise females of reproductive potential of the potential risk to the fetus, and to use effective contraception. (5.10, 8.1)
- Growth Retardation in Children and Adolescents: Growth retardation occurring in children and pre-adolescents receiving Imkeldi has been reported. Close monitoring of growth in children under Imkeldi treatment is recommended. (5.11, 6.2)
- Tumor Lysis Syndrome: Close monitoring is recommended. (5.12)
- Impairments Related to Driving and Using Machinery: Motor vehicle accidents have been reported in patients receiving imatinib. Caution patients about driving a car or operating machinery. (5.13)
- Renal Toxicity: A decline in renal function may occur in patients receiving Imkeldi. Evaluate renal function at baseline and during therapy, with attention to risk factors for renal dysfunction. (5.14)
- Measuring Device: Advise patients to measure IMKELDI with an accurate milliliter measuring device. Inform patients that a household teaspoon is not an accurate measuring device and could lead to overdosage, which can result in serious adverse reactions. Advise patients to ask their pharmacist to recommend an appropriate press-in bottle adapter and oral dispensing syringe and for instructions for measuring the correct dose. (5.15)

6 ADVERSE REACTIONS

The most frequently reported adverse reactions (≥30%) are edema, nausea, vomiting, muscle cramps, musculoskeletal pain, diarrhea, rash, fatigue, and abdominal pain. (6.1)

To report SUSPECTED ADVERSE REACTIONS, contact Shorla Oncology at 844-9-SHORLA or FDA at 1-800-FDA-1088 or www.fda.gov/medwatch.

7 DRUG INTERACTIONS

• CYP3A4 inducers: Avoid or increase imatinib dosage if unavoidable. (7.1)
• CYP3A4 inhibitors: Use caution. Avoid grapefruit juice. (7.2)
• CYP3A4 substrates: Use caution. Patients who require anticoagulation should receive other anticoagulants instead of warfarin. (7.3)
• CYP2D6 substrates: Use caution. (7.4)

8 USE IN SPECIFIC POPULATIONS

- Lactation: Advise not to breastfeed.(8.2)

FULL PRESCRIBING INFORMATION

1 INDICATIONS AND USAGE

1.1 Newly Diagnosed Philadelphia Positive Chronic Myeloid Leukemia (Ph+ CML)

Newly diagnosed adult and pediatric patients with Philadelphia chromosome positive chronic myeloid leukemia (Ph+ CML) in chronic phase.

1.2 Ph+ CML in Blast Crisis (BC), Accelerated Phase (AP) or Chronic Phase (CP) After Interferon-alpha (IFN) Therapy

Patients with Philadelphia chromosome positive chronic myeloid leukemia in blast crisis, accelerated phase, or in chronic phase after failure of interferon-alpha therapy.

1.3 Adult Patients With Ph+ Acute Lymphoblastic Leukemia (ALL)

Adult patients with relapsed or refractory Philadelphia chromosome positive acute lymphoblastic leukemia (Ph+ ALL).

1.4 Pediatric Patients With Ph+ Acute Lymphoblastic Leukemia (ALL)

Pediatric patients with newly diagnosed Philadelphia chromosome positive acute lymphoblastic leukemia (Ph+ ALL) in combination with chemotherapy.

1.5 Myelodysplastic/Myeloproliferative Diseases (MDS/MPD)

Adult patients with myelodysplastic/myeloproliferative diseases associated with platelet-derived growth factor receptor (PDGFR) gene re-arrangements.

1.6 Aggressive Systemic Mastocytosis (ASM)

Adult patients with aggressive systemic mastocytosis without the D816V c-Kit mutation or with c-Kit mutational status unknown.

1.7 Hypereosinophilic Syndrome (HES) and/or Chronic Eosinophilic Leukemia (CEL)

Adult patients with hypereosinophilic syndrome and/or chronic eosinophilic leukemia who have the FIP1L1-PDGFRα fusion kinase (mutational analysis or fluorescence in situ hybridization [FISH] demonstration of CHIC2 allele deletion) and for patients with HES and/or CEL who are FIP1L1-PDGFRα fusion kinase negative or unknown.

1.8 Dermatofibrosarcoma Protuberans (DFSP)

Adult patients with unresectable, recurrent and/or metastatic dermatofibrosarcoma protuberans.

1.9 Kit+ Gastrointestinal Stromal Tumors (GIST)

Patients with Kit (CD117) positive unresectable and/or metastatic malignant gastrointestinal stromal tumors.

1.10 Adjuvant Treatment of GIST

Adjuvant treatment of adult patients following complete gross resection of Kit (CD117) positive GIST.

2 DOSAGE AND ADMINISTRATION

2.1 Important Administration Instructions

All doses of Imkeldi should be taken with a meal and a large glass of water. Doses of 400 mg or 600 mg should be administered once daily, and a dose of 800 mg should be administered as 400 mg twice a day. If a dose is missed, the patient should wait until the next scheduled dose and not take two doses at the same time.

Imkeldi is intended for oral use only. It is important that Imkeldi be measured with an accurate measuring device [see Warnings and Precautions (5.15), Instructions for Use]. A household teaspoon is not an accurate measuring device. A pharmacist can provide a press-in bottle adapter and oral dispensing syringe and can provide instructions for measuring the correct dose.

Recommendations for Dose Rounding

Round each dose to the nearest measurable graduation mark on the oral syringe, if necessary [see Instructions for Use].

Continue treatment until disease progression or unacceptable toxicity.

Imkeldi is a hazardous drug. Follow applicable special handling and disposal procedures^1.

2.2 Adult Patients With Ph+ CML CP, AP, or BC

The recommended dosage of Imkeldi is 400 mg/day for adult patients in chronic phase CML and 600 mg/day for adult patients in accelerated phase or blast crisis.

In CML, a dose increase from 400 mg to 600 mg in adult patients with chronic phase disease, or from 600 mg to 800 mg (given as 400 mg twice daily) in adult patients in accelerated phase or blast crisis may be considered in the absence of severe adverse drug reaction and severe non-leukemia related neutropenia or thrombocytopenia in the following circumstances: disease progression (at any time), failure to achieve a satisfactory hematologic response after at least 3 months of treatment, failure to achieve a cytogenetic response after 6 to 12 months of treatment, or loss of a previously achieved hematologic or cytogenetic response.

2.3 Pediatric Patients With Ph+ CML CP

The recommended dosage of Imkeldi for pediatric patients with newly diagnosed Ph+ CML is 340 mg/m^2/day (not to exceed 600 mg). Imkeldi treatment can be given as a once daily dose or the daily dose may be split into two–one portion doses in the morning and one portion in the evening. There is no experience with Imkeldi treatment in children under 1 year of age.

Follow recommendations for dose rounding [see Dosage and Administration (2.1)].

2.4 Adult Patients With Ph+ ALL

The recommended dosage of Imkeldi is 600 mg/day for adult patients with relapsed/refractory Ph+ ALL.

2.5 Pediatric Patients With Ph+ ALL

The recommended dosage of Imkeldi to be given in combination with chemotherapy to pediatric patients with newly diagnosed Ph+ ALL is 340 mg/m^2/day (not to exceed 600 mg). Imkeldi treatment can be given as a once daily dose.

Follow recommendations for dose rounding [see Dosage and Administration (2.1)].

2.6 Adult Patients With MDS/MPD

Determine PDGFRb gene rearrangements status prior to initiating treatment.

The recommended dosage of Imkeldi is 400 mg/day for adult patients with MDS/MPD.

2.7 Adult Patients With ASM

Determine D816V c-Kit mutation status prior to initiating treatment.

The recommended dosage of Imkeldi is 400 mg/day for adult patients with ASM without the D816V c-Kit mutation. If c- Kit mutational status is not known or unavailable, treatment with Imkeldi 400 mg/day may be considered for patients with ASM not responding satisfactorily to other therapies. For patients with ASM associated with eosinophilia, a clonal hematological disease related to the fusion kinase FIP1L1-PDGFRα, a starting dose of 100 mg/day is recommended. Dose increase from 100 mg to 400 mg for these patients may be considered in the absence of adverse drug reactions if assessments demonstrate an insufficient response to therapy.

2.8 Adult Patients With HES/CEL

The recommended dosage of Imkeldi is 400 mg/day for adult patients with HES/CEL. For HES/CEL patients with demonstrated FIP1L1-PDGFRα fusion kinase, a starting dose of 100 mg/day is recommended. Dose increase from 100 mg to 400 mg for these patients may be considered in the absence of adverse drug reactions if assessments demonstrate an insufficient response to therapy.

2.9 Adult Patients With DFSP

The recommended dosage of Imkeldi is 800 mg/day for adult patients with DFSP.

2.10 Adult Patients With Metastatic and/or Unresectable GIST

The recommended dosage of Imkeldi is 400 mg/day for adult patients with unresectable and/or metastatic, malignant GIST. A dose increase up to 800 mg daily (given as 400 mg twice daily) may be considered, as clinically indicated, in patients showing clear signs or symptoms of disease progression at a lower dose and in the absence of severe adverse drug reactions.

2.11 Adult Patients With Adjuvant GIST

The recommended dosage of Imkeldi is 400 mg/day for the adjuvant treatment of adult patients following complete gross resection of GIST. In clinical trials, one year of imatinib and three years of imatinib were studied. In the patient population defined in Study 2, three years of Imkeldi is recommended [see Clinical Studies (14.8)]. The optimal treatment duration with Imkeldi is not known.

2.12 Dosage Modifications for Drug Interactions, Hepatic Impairment, and Renal Impairment

Drug Interactions

Concomitant Strong CYP3A4 inducers

Avoid concomitant use of strong CYP3A4 inducers (e.g., dexamethasone, phenytoin, carbamazepine, rifampin, rifabutin, rifampacin, phenobarbital) with Imkeldi. If concomitant use with a strong CYP3A4 inducer cannot be avoided the Imkeldi dosage should be increased by at least 50%, and clinical response should be carefully monitored [see Drug Interactions (7.1)].

Hepatic Impairment

A 25% decrease in the approved recommended Imkeldi dosage should be used for patients with severe hepatic impairment (total bilirubin ˃3 to 10 times upper limit of normal [ULN] and any value for AST) [see Use in Specific Populations (8.6)].

Patients with mild hepatic impairment (total bilirubin ≤ ULN and aspartate aminotransferase [AST] > ULN, or total bilirubin ˃1 to 1.5 times ULN and any value for AST) and moderate hepatic impairment (total bilirubin ˃ 1.5 to 3 times ULN and any value for AST) do not require a dose adjustment and should be treated per the approved recommended dosage.

Renal Impairment

Imkeldi should be used with caution in patients with severe renal impairment [see Warnings and Precautions (5.3), Use in Specific Populations (8.7)].

Patients with moderate renal impairment (creatinine clearance [CLcr] = 20-39 mL/min) should receive a 50% decrease in the recommended starting dose and future doses can be increased as tolerated. Doses greater than 600 mg are not recommended in patients with mild renal impairment (CLcr = 40-59 mL/min). Doses greater than 400 mg are not recommended for patients with moderate renal impairment.

2.13 Dosage Modifications for Hepatotoxicity and Non-Hematologic Adverse Reactions

If elevations in bilirubin greater than 3 times the institutional upper limit of normal (IULN) or in liver transaminases greater than 5 times the IULN occur, Imkeldi should be withheld until bilirubin levels have returned to a less than 1.5 times the IULN and transaminase levels to less than 2.5 times the IULN. In adults, treatment with Imkeldi may then be continued at a reduced daily dose (i.e., 400 mg to 300 mg, 600 mg to 400 mg, or 800 mg to 600 mg). In children, daily doses can be reduced under the same circumstances from 340 mg/m^2/day to 260 mg/m^2/day.

If a severe non-hematologic adverse reaction develops (such as severe hepatotoxicity or severe fluid retention), Imkeldi should be withheld until the event has resolved. Thereafter, treatment can be resumed as appropriate depending on the initial severity of the reaction.

2.14 Dosage Modifications for Hematologic Adverse Reactions

Dose reduction or treatment interruptions for severe neutropenia and thrombocytopenia are recommended as indicated in Table 1.

Table 1: Dose Adjustments for Neutropenia and Thrombocytopenia
ASM associated with eosinophilia (starting dose 100 mg) | ANC less than 1 x 10^9/L and/or; platelets less than 50 x 10^9/L | 1. Stop Imkeldi until ANC greater than or equal to 1.5 x 10^9/L and platelets greater than or equal to 75 x 10^9/L 2. Resume treatment with Imkeldi at previous dose (i.e., dose before severe adverse reaction)
HES/CEL with FIP1L1-PDGFRα; fusion kinase (starting dose 100 mg) | ANC less than 1 x 10^9/L and/or; platelets less than 50 x 10^9/L | 1. Stop Imkeldi until ANC greater than or equal to 1.5 x 10^9/L and platelets greater than or equal to 75 x 10^9/L 2. Resume treatment with Imkeldi at previous dose (i.e., dose before severe adverse reaction)
Chronic Phase CML (starting dose 400 mg); MDS/MPD, ASM and HES/CEL; (starting dose 400 mg); GIST (starting dose 400 mg) | ANC less than 1 x 10^9/L and/or; platelets less than 50 x 10^9/L | 1. Stop Imkeldi until ANC greater than or equal to 1.5 x 10^9/L and platelets greater than or equal to 75 x 10^9/L 2. Resume treatment with Imkeldi at the original starting dose of 400 mg 3. If recurrence of ANC less than 1 x 10^9/L and/or platelets less than 50 x 10^9/L, repeat step 1 and resume Imkeldi at a reduced dose of 300 mg
Ph+ CML: Accelerated Phase and Blast Crisis (starting dose 600 mg); Ph+ ALL; (starting dose 600 mg) | ANC less than 0.5 x 10^9/L and/or; platelets less than 10 x 10^9/L | 1. Check if cytopenia is related to leukemia (marrow aspirate or biopsy) 2. If cytopenia is unrelated to leukemia, reduce dose of Imkeldi to 400 mg 3. If cytopenia persists 2 weeks, reduce further to 300 mg 4. If cytopenia persists 4 weeks and is still unrelated to leukemia, stop Imkeldi until ANC greater than or equal to 1 x 10^9/L and platelets greater than or equal to 20 x 10^9/L and then resume treatment at 300 mg
DFSP; (starting dose 800 mg) | ANC less than 1 x 10^9/L and/or; platelets less than 50 x 10^9/L | 1. Stop Imkeldi until ANC greater than or equal to 1.5 x 10^9/L and platelets greater than or equal to 75 x 10^9/L 2. Resume treatment with Imkeldi at 600 mg 3. In the event of recurrence of ANC less than 1 x 10^9/L and/or platelets less than 50 x 10^9/L, repeat step 1 and resume Imkeldi at reduced dose of 400 mg
Pediatric newly diagnosed chronic phase CML; (starting dose 340 mg/m^2) | ANC less than 1 x 10^9/L and/or; platelets less than 50 x 10^9/L | 1. Stop Imkeldi until ANC greater than or equal to 1.5 x 10^9/L and platelets greater than or equal to 75 x 10^9/L 2. Resume treatment with Imkeldi at previous dose (i.e., dose before severe adverse reaction) 3. In the event of recurrence of ANC less than 1 x 10^9/L and/or platelets less than 50 x 10^9/L, repeat step 1 and resume Imkeldi at reduced dose of 260 mg/m^2

Abbreviations: ANC, absolute neutrophil count; ASM, aggressive systemic mastocytosis; CEL, chronic eosinophilic leukemia; CML, chronic myeloid leukemia; DFSP, dermatofibrosarcoma protuberans; HES, hypereosinophilic syndrome; MDS/MPD, myelodysplastic/myeloproliferative diseases; PDGFR, platelet-derived growth factor receptor; Ph+ CML, Philadelphia chromosome positive chronic myeloid leukemia; Ph+ ALL, Philadelphia chromosome positive acute lymphoblastic leukemia.

3 DOSAGE FORMS AND STRENGTHS

Oral solution: 80 mg/mL imatinib as 140 mL of a clear yellow to brownish yellow colored solution with a strawberry flavor.

4 CONTRAINDICATIONS

None.

5 WARNINGS AND PRECAUTIONS

5.1 Fluid Retention and Edema

Imatinib can cause edema and occasionally serious fluid retention [see Adverse Reactions (6.1)]. Weigh and monitor patients regularly for signs and symptoms of fluid retention. Investigate unexpected rapid weight gain carefully and provide appropriate treatment. The probability of edema was increased with higher imatinib dose and age greater than 65 years in the CML studies. Severe superficial edema was reported in 1.5% of newly diagnosed CML patients taking imatinib, and in 2% to 6% of other adult CML patients taking imatinib. In addition, other severe fluid retention (e.g., pleural effusion, pericardial effusion, pulmonary edema, and ascites) reactions were reported in 1.3% of newly diagnosed CML patients taking imatinib, and in 2% to 6% of other adult CML patients taking imatinib. Severe fluid retention was reported in 9% to 13.1% of patients taking imatinib for GIST [see Adverse Reactions (6.1)]. In a randomized trial in patients with newly diagnosed Ph+ CML in chronic phase comparing imatinib and nilotinib, severe (Grade 3 or 4) fluid retention occurred in 2.5% of patients receiving imatinib and in 3.9% of patients receiving nilotinib 300 mg twice daily.

Effusions (including pleural effusion, pericardial effusion, ascites) or pulmonary edema were observed in 2.1% (none were Grade 3 or 4) of patients in the imatinib arm and 2.2% (0.7% Grade 3 or 4) of patients in the nilotinib 300 mg twice daily arm.

5.2 Hematologic Toxicity

Treatment with imatinib can cause anemia, neutropenia, and thrombocytopenia. Perform complete blood counts weekly for the first month, biweekly for the second month, and periodically thereafter as clinically indicated (for example, every 2 to 3 months). In CML, the occurrence of these cytopenias is dependent on the stage of disease and is more frequent in patients with accelerated phase CML or blast crisis than in patients with chronic phase CML. In pediatric CML patients the most frequent toxicities observed were Grade 3 or 4 cytopenias, including neutropenia, thrombocytopenia, and anemia. These generally occur within the first several months of therapy [see Dosage and Administration (2.14)].

5.3 Congestive Heart Failure and Left Ventricular Dysfunction

Congestive heart failure and left ventricular dysfunction have been reported in patients taking imatinib. Cardiac adverse reactions were more frequent in patients with advanced age or co-morbidities, including previous medical history of cardiac disease. In an international randomized Phase 3 study in 1106 patients with newly diagnosed Ph+ CML in chronic phase, severe cardiac failure and left ventricular dysfunction were observed in 0.7% of patients taking imatinib compared to 0.9% of patients taking IFN + Ara-C. In another randomized trial with newly diagnosed Ph+ CML patients in chronic phase that compared imatinib and nilotinib, cardiac failure was observed in 1.1% of patients in the imatinib arm and 2.2% of patients in the nilotinib 300 mg twice daily arm and severe (Grade 3 or 4) cardiac failure occurred in 0.7% of patients in each group. Carefully monitor patients with cardiac disease or risk factors for cardiac or history of renal failure.

Evaluate and treat any patient with signs or symptoms consistent with cardiac or renal failure.

5.4 Hepatotoxicity

Hepatotoxicity, occasionally severe, may occur with Imkeldi [see Adverse Reactions (6.1)]. Cases of fatal liver failure and severe liver injury requiring liver transplants have been reported with both short-term and long-term use of imatinib. Monitor liver function (transaminases, bilirubin, and alkaline phosphatase) before initiation of treatment and monthly, or as clinically indicated. Manage laboratory abnormalities with Imkeldi interruption and/or dose reduction [see Dosage and Administration (2.13)]. When imatinib is combined with chemotherapy, liver toxicity in the form of transaminase elevation and hyperbilirubinemia has been observed. Additionally, there have been reports of acute liver failure.

Monitoring of hepatic function is recommended.

5.5 Hemorrhage

In a trial of imatinib versus IFN+Ara-C in patients with the newly diagnosed CML, 1.8% of patients had Grade 3/4 hemorrhage. In the Phase 3 unresectable or metastatic GIST studies, 211 patients (12.9%) reported Grade 3/4 hemorrhage at any site. In the Phase 2 unresectable or metastatic GIST study, 7 patients (5%) had a total of 8 CTC Grade 3/4 hemorrhages; gastrointestinal (GI) (3 patients), intra-tumoral (3 patients) or both (1 patient). Gastrointestinal tumor sites may have been the source of GI hemorrhages. In a randomized trial in patients with newly diagnosed Ph+ CML in chronic phase comparing imatinib and nilotinib, GI hemorrhage occurred in 1.4% of patients in the imatinib arm, and in 2.9% of patients in the nilotinib 300 mg twice daily arm. None of these events were Grade 3 or 4 in the imatinib arm; 0.7% were Grade 3 or 4 in the nilotinib 300 mg twice daily arm. In addition, gastric antral vascular ectasia has been reported in postmarketing experience.

5.6 Gastrointestinal Disorders

Imatinib can cause GI irritation. Imkeldi should be taken with food and a large glass of water to minimize this problem. There have been rare reports, including fatalities, of GI perforation.

5.7 Hypereosinophilic Cardiac Toxicity

In patients with hypereosinophilic syndrome with occult infiltration of HES cells within the myocardium, cases of cardiogenic shock/left ventricular dysfunction have been associated with HES cell degranulation upon the initiation of Imkeldi therapy. The condition was reported to be reversible with the administration of systemic steroids, circulatory support measures and temporarily withholding Imkeldi.

Myelodysplastic/myeloproliferative disease and systemic mastocytosis may be associated with high eosinophil levels. Consider performing an echocardiogram and determining serum troponin in patients with HES/CEL, and in patients with MDS/MPD or ASM associated with high eosinophil levels. If either is abnormal, consider prophylactic use of systemic steroids (1-2 mg/kg) for one to two weeks concomitantly with Imkeldi at the initiation of therapy.

5.8 Dermatologic Toxicities

Bullous dermatologic reactions, including erythema multiforme and Stevens-Johnson syndrome, have been reported with use of imatinib. In some cases of bullous dermatologic reactions, including erythema multiforme and Stevens-Johnson syndrome reported during postmarketing surveillance, a recurrent dermatologic reaction was observed upon rechallenge. Several foreign postmarketing reports have described cases in which patients tolerated the reintroduction of imatinib therapy after resolution or improvement of the bullous reaction. In these instances, imatinib was resumed at a dose lower than that at which the reaction occurred and some patients also received concomitant treatment with corticosteroids or antihistamines.

5.9 Hypothyroidism

Clinical cases of hypothyroidism have been reported in thyroidectomy patients undergoing levothyroxine replacement during treatment with imatinib. Monitor TSH levels in such patients.

5.10 Embryo-Fetal Toxicity

Imkeldi can cause fetal harm when administered to a pregnant woman. Imatinib mesylate was teratogenic in rats when administered during organogenesis at doses approximately equal to the maximum human dose of 800 mg/day based on body surface area (BSA). Significant post-implantation loss was seen in female rats administered imatinib mesylate at doses approximately one-half the maximum human dose of 800 mg/day based on BSA. Advise females of reproductive potential to use effective contraception (methods that result in less than 1% pregnancy rates) when using Imkeldi and for 14 days after stopping Imkeldi. Advise pregnant women of the potential risk to a fetus [see Use in Specific Populations (8.1)].

5.11 Growth Retardation in Children and Adolescents

Growth retardation has been reported in children and pre-adolescents receiving imatinib. The long-term effects of prolonged treatment with Imkeldi on growth in children are unknown. Therefore, monitor growth in children under Imkeldi treatment [see Adverse Reactions (6.1)].

5.12 Tumor Lysis Syndrome

Cases of Tumor Lysis Syndrome (TLS), including fatal cases, have been reported in patients with CML, GIST, ALL, and eosinophilic leukemia receiving imatinib. The patients at risk of TLS are those with tumors having a high proliferative rate or high tumor burden prior to treatment. Monitor these patients closely and take appropriate precautions. Due to possible occurrence of TLS, correct clinically significant dehydration and treat high uric acid levels prior to initiation of Imkeldi.

5.13 Impairments Related to Driving and Using Machinery

Motor vehicle accidents have been reported in patients receiving imatinib. Advise patients that they may experience side effects, such as dizziness, blurred vision, or somnolence during treatment with Imkeldi. Recommend caution when driving a car or operating machinery.

5.14 Renal Toxicity

A decline in renal function may occur in patients receiving Imkeldi. Median estimated glomerular filtration rate (eGFR) values in patients on imatinib 400 mg daily for newly-diagnosed CML (four randomized trials) and malignant GIST (one single-arm trial) declined from a baseline value of 85 mL/min/1.73 m^2 (N = 1190) to 75 mL/min/1.73 m^2 at 12 months (N = 1082) and 69 mL/min/1.73 m^2 at 60 months (N = 549). Evaluate renal function prior to initiating Imkeldi and monitor during therapy, with attention to risk factors for renal dysfunction, such as preexisting renal impairment, diabetes mellitus, hypertension, and congestive heart failure.

5.15 Measuring Device

Advise patients to measure Imkeldi with an accurate milliliter measuring device. Inform patients that a household teaspoon is not an accurate measuring device and could lead to overdosage, which can result in serious adverse reactions. Advise patients to ask their pharmacist to recommend an appropriate press-in bottle adapter and oral dispensing syringe and for instructions for measuring the correct dose [see Instructions for Use].

6 ADVERSE REACTIONS

The following serious adverse reactions are described elsewhere in the labeling:

- Fluid Retention and Edema [see Warnings and Precautions (5.1)]
- Hematologic Toxicity [see Warnings and Precautions (5.2)]
- Congestive Heart Failure and Left Ventricular Dysfunction [see Warnings and Precautions (5.3)]
- Hepatotoxicity [see Warnings and Precautions (5.4)]
- Hemorrhage [see Warnings and Precautions (5.5)]
- Gastrointestinal Disorders [see Warnings and Precautions (5.6)]
- Hypereosinophilic Cardiac Toxicity [see Warnings and Precautions (5.7)]
- Dermatologic Toxicities [see Warnings and Precautions (5.8)]
- Hypothyroidism [see Warnings and Precautions (5.9)]
- Growth Retardation in Children and Adolescents [see Warnings and Precautions (5.11)]
- Tumor Lysis Syndrome [see Warnings and Precautions (5.12)]
- Impairments Related to Driving and Using Machinery [see Warnings and Precautions (5.13)]
- Renal Toxicity [see Warnings and Precautions (5.14)]

6.1 Clinical Trials Experience

Because clinical trials are conducted under widely varying conditions, adverse reaction rates observed in the clinical trials of a drug cannot be directly compared to rates in the clinical trials of another drug and may not reflect the rates observed in practice.

Chronic Myeloid Leukemia

The majority of imatinib-treated patients experienced adverse reactions at some time. Imatinib was discontinued due to drug-related adverse reactions in 2.4% of patients receiving imatinib in the randomized trial of newly diagnosed patients with Ph+ CML in chronic phase comparing imatinib versus IFN+Ara-C, and in 12.5% of patients receiving imatinib in the randomized trial of newly diagnosed patients with Ph+ CML in chronic phase comparing imatinib and nilotinib. Imatinib was discontinued due to drug-related adverse reactions in 4% of patients in chronic phase after failure of interferon-alpha therapy, in 4% of patients in accelerated phase and in 5% of patients in blast crisis.

The most frequently reported drug-related adverse reactions were edema, nausea and vomiting, muscle cramps, musculoskeletal pain, diarrhea and rash (Table 2 and Table 3 for newly diagnosed CML, Table 4 for other CML patients). Edema was most frequently periorbital or in lower limbs and was managed with diuretics, other supportive measures, or by reducing the dose of imatinib [see Dosage and Administration (2.13)]. The frequency of severe superficial edema was 1.5%-6%.

A variety of adverse reactions represent local or general fluid retention, including pleural effusion, ascites, pulmonary edema, and rapid weight gain with or without superficial edema. These reactions appear to be dose related, were more common in the blast crisis and accelerated phase studies (where the dose was 600 mg/day), and are more common in the elderly. These reactions were usually managed by interrupting imatinib treatment and using diuretics or other appropriate supportive care measures. These reactions may be serious or life threatening.

Adverse reactions, regardless of relationship to study drug, that were reported in at least 10% of the imatinib-treated patients are shown in Tables 2, 3, and 4.

Table 2: Adverse Reactions Regardless of Relationship to Study Drug Reported in Newly Diagnosed CML Clinical Trial in the Imatinib Versus IFN+Ara-C Study (Greater Than or Equal to 10% of Imatinib-Treated Patients) [All adverse reactions occurring in greater than or equal to 10% of imatinib-treated patients are listed regardless of suspected relationship to treatment.]
 | All Grades |  | CTC Grades [NCI Common Terminology Criteria for Adverse Events, version 3.0.] 3/4
Preferred term | Imatinib N = 551 (%) | IFN+Ara-C N = 533 (%) | Imatinib N = 551 (%) | IFN+Ara-C N = 533 (%)
Fluid retention | 61.7 | 11.1 | 2.5 | 0.9
- Superficial edema | 59.9 | 9.6 | 1.5 | 0.4
- Other fluid retention reactions [Other fluid retention reactions include pleural effusion, ascites, pulmonary edema, pericardial effusion, anasarca, edema aggravated, and fluid retention not otherwise specified.] | 6.9 | 1.9 | 1.3 | 0.6
Nausea | 49.5 | 61.5 | 1.3 | 5.1
Muscle cramps | 49.2 | 11.8 | 2.2 | 0.2
Musculoskeletal pain | 47.0 | 44.8 | 5.4 | 8.6
Diarrhea | 45.4 | 43.3 | 3.3 | 3.2
Rash and related terms | 40.1 | 26.1 | 2.9 | 2.4
Fatigue | 38.8 | 67.0 | 1.8 | 25.1
Headache | 37.0 | 43.3 | 0.5 | 3.8
Joint pain | 31.4 | 38.1 | 2.5 | 7.7
Abdominal pain | 36.5 | 25.9 | 4.2 | 3.9
Nasopharyngitis | 30.5 | 8.8 | 0 | 0.4
Hemorrhage | 28.9 | 21.2 | 1.8 | 1.7
- GI hemorrhage | 1.6 | 1.1 | 0.5 | 0.2
- CNS hemorrhage | 0.2 | 0.4 | 0 | 0.4
Myalgia | 24.1 | 38.8 | 1.5 | 8.3
Vomiting | 22.5 | 27.8 | 2.0 | 3.4
Dyspepsia | 18.9 | 8.3 | 0 | 0.8
Cough | 20.0 | 23.1 | 0.2 | 0.6
Pharyngolaryngeal pain | 18.1 | 11.4 | 0.2 | 0
Upper respiratory tract infection | 21.2 | 8.4 | 0.2 | 0.4
Dizziness | 19.4 | 24.4 | 0.9 | 3.8
Pyrexia | 17.8 | 42.6 | 0.9 | 3.0
Weight increased | 15.6 | 2.6 | 2.0 | 0.4
Insomnia | 14.7 | 18.6 | 0 | 2.3
Depression | 14.9 | 35.8 | 0.5 | 13.1
Influenza | 13.8 | 6.2 | 0.2 | 0.2
Bone pain | 11.3 | 15.6 | 1.6 | 3.4
Constipation | 11.4 | 14.4 | 0.7 | 0.2
Sinusitis | 11.4 | 6.0 | 0.2 | 0.2
Abbreviations: CML, chronic myeloid leukemia; CNS, central nervous system; CTC, common terminology criteria; GI, gastrointestinal; IFN, Interferon-alpha.

Table 3: Most Frequently Reported Non-Hematologic Adverse Reactions (regardless of relationship to study drug) in Patients With Newly Diagnosed Ph+ CML-CP in the Imatinib Versus Nilotinib Study (Greater Than or Equal to 10% in Imatinib 400 mg Once Daily or Nilotinib 300 mg Twice Daily Groups) 60-Month Analysis [Excluding laboratory abnormalities.]
Patients with newly diagnosed Ph+ CML-CP
 |  | Imatinib; 400 mg; once daily; N = 280 | Nilotinib; 300 mg; twice daily; N = 279 | Imatinib; 400 mg; once daily; N = 280 | Nilotinib; 300 mg; twice daily; N = 279
Body system and preferred term |  | All Grades (%) |  | CTC Grades [NCI Common Terminology Criteria for Adverse Events, version 3.0.] 3/4 (%)
Skin and subcutaneous tissue disorders | Rash | > 19 | 38 | 2 | < 1
 | Pruritus | 7 | 21 | 0 | < 1
 | Alopecia | 7 | 13 | 0 | 0
 | Dry skin | 6 | 12 | 0 | 0
Gastrointestinal disorders | Nausea | 41 | 22 | 2 | 2
 | Constipation | 8 | 20 | 0 | < 1
 | Diarrhea | 46 | 19 | 4 | 1
 | Vomiting | 27 | 15 | < 1 | < 1
 | Abdominal pain upper | 14 | 18 | < 1 | 1
 | Abdominal pain | 12 | 15 | 0 | 2
 | Dyspepsia | 12 | 10 | 0 | 0
Nervous system disorders | Headache | 23 | 32 | < 1 | 3
 | Dizziness | 11 | 12 | < 1 | < 1
General disorders and administration-site conditions | Fatigue | 20 | 23 | 1 | 1
 | Pyrexia | 13 | 14 | 0 | < 1
 | Asthenia | 12 | 14 | 0 | < 1
 | Peripheral edema | 20 | 9 | 0 | < 1
 | Face edema | 14 | < 1 | < 1 | 0
Musculoskeletal and connective tissue disorders | Myalgia | 19 | 19 | < 1 | < 1
 | Arthralgia | 17 | 22 | < 1 | < 1
 | Muscle spasms | 34 | 12 | 1 | 0
 | Pain in extremity | 16 | 15 | < 1 | < 1
 | Back pain | 17 | 19 | 1 | 1
Respiratory, thoracic and mediastinal disorders | Cough | 13 | 17 | 0 | 0
 | Oropharyngeal pain | 6 | 12 | 0 | 0
 | Dyspnea | 6 | 11 | < 1 | 2
Infections and infestations | Nasopharyngitis | 21 | 27 | 0 | 0
 | Upper respiratory tract infection | 14 | 17 | 0 | < 1
 | Influenza | 9 | 13 | 0 | 0
 | Gastroenteritis | 10 | 7 | < 1 | 0
Eye disorders | Eyelid edema | 19 | 1 | < 1 | 0
 | Periorbital edema | 15 | < 1 | 0 | 0
Psychiatric disorders | Insomnia | 9 | 11 | 0 | 0
Vascular disorder | Hypertension | 4 | 10 | < 1 | 1
Abbreviation: Ph+ CML-CP, Philadelphia chromosome positive chronic myeloid leukemia-chronic phase.

Table 4: Adverse Reactions Regardless of Relationship to Study Drug Reported in Other CML Clinical Trials (Greater Than or Equal to 10% of All Patients in Any Trial) [All adverse reactions occurring in greater than or equal to 10% of patients are listed regardless of suspected relationship to treatment.]
 | Myeloid blast Crisis (n = 260) |  | Accelerated phase; (n = 235) |  | Chronic phase, IFN failure; (n = 532)
 | % |  | % |  | %
Preferred term | All Grades | Grade 3/4 | All Grades | Grade 3/4 | All Grades | Grade 3/4
Fluid retention | 72 | 11 | 76 | 6 | 69 | 4
-Superficial edema | 66 | 6 | 74 | 3 | 67 | 2
-Other fluid retention reactions [Other fluid retention reactions include pleural effusion, ascites, pulmonary edema, pericardial effusion, anasarca, edema aggravated, and fluid retention not otherwise specified.] | 22 | 6 | 15 | 4 | 7 | 2
Nausea | 71 | 5 | 73 | 5 | 63 | 3
Muscle cramps | 28 | 1 | 47 | 0.4 | 62 | 2
Vomiting | 54 | 4 | 58 | 3 | 36 | 2
Diarrhea | 43 | 4 | 57 | 5 | 48 | 3
Hemorrhage | 53 | 19 | 49 | 11 | 30 | 2
- CNS hemorrhage | 9 | 7 | 3 | 3 | 2 | 1
- GI hemorrhage | 8 | 4 | 6 | 5 | 2 | 0.4
Musculoskeletal pain | 42 | 9 | 49 | 9 | 38 | 2
Fatigue | 30 | 4 | 46 | 4 | 48 | 1
Skin rash | 36 | 5 | 47 | 5 | 47 | 3
Pyrexia | 41 | 7 | 41 | 8 | 21 | 2
Arthralgia | 25 | 5 | 34 | 6 | 40 | 1
Headache | 27 | 5 | 32 | 2 | 36 | 0.6
Abdominal pain | 30 | 6 | 33 | 4 | 32 | 1
Weight increased | 5 | 1 | 17 | 5 | 32 | 7
Cough | 14 | 0.8 | 27 | 0.9 | 20 | 0
Dyspepsia | 12 | 0 | 22 | 0 | 27 | 0
Myalgia | 9 | 0 | 24 | 2 | 27 | 0.2
Nasopharyngitis | 10 | 0 | 17 | 0 | 22 | 0.2
Asthenia | 18 | 5 | 21 | 5 | 15 | 0.2
Dyspnea | 15 | 4 | 21 | 7 | 12 | 0.9
Upper respiratory tract infection | 3 | 0 | 12 | 0.4 | 19 | 0
Anorexia | 14 | 2 | 17 | 2 | 7 | 0
Night sweats | 13 | 0.8 | 17 | 1 | 14 | 0.2
Constipation | 16 | 2 | 16 | 0.9 | 9 | 0.4
Dizziness | 12 | 0.4 | 13 | 0 | 16 | 0.2
Pharyngitis | 10 | 0 | 12 | 0 | 15 | 0
Insomnia | 10 | 0 | 14 | 0 | 14 | 0.2
Pruritus | 8 | 1 | 14 | 0.9 | 14 | 0.8
Hypokalemia | 13 | 4 | 9 | 2 | 6 | 0.8
Pneumonia | 13 | 7 | 10 | 7 | 4 | 1
Anxiety | 8 | 0.8 | 12 | 0 | 8 | 0.4
Liver toxicity | 10 | 5 | 12 | 6 | 6 | 3
Rigors | 10 | 0 | 12 | 0.4 | 10 | 0
Chest pain | 7 | 2 | 10 | 0.4 | 11 | 0.8
Influenza | 0.8 | 0.4 | 6 | 0 | 11 | 0.2
Sinusitis | 4 | 0.4 | 11 | 0.4 | 9 | 0.4
Abbreviations: CML, chronic myeloid leukemia; IFN, Interferon-alpha.

Hematologic and Biochemistry Laboratory Abnormalities

Cytopenias, and particularly neutropenia and thrombocytopenia, were a consistent finding in all studies, with a higher frequency at doses greater than or equal to 750 mg (Phase 1 study). The occurrence of cytopenias in CML patients was also dependent on the stage of the disease.

In patients with newly diagnosed CML, cytopenias were less frequent than in the other CML patients (see Tables 5, 6, and 7). The frequency of Grade 3 or 4 neutropenia and thrombocytopenia was between 2- and 3-fold higher in blast crisis and accelerated phase compared to chronic phase (see Tables 4 and 5). The median duration of the neutropenic and thrombocytopenic episodes varied from 2 to 3 weeks, and from 2 to 4 weeks, respectively.

These reactions can usually be managed with either a reduction of the dose or an interruption of treatment with imatinib, but may require permanent discontinuation of treatment.

Table 5: Laboratory Abnormalities in Newly Diagnosed CML Clinical Trial (Imatinib Versus IFN+Ara-C)
 | Imatinib; N = 551 |  | IFN+Ara-C; N = 533
 | % |  | %
CTC Grades | Grade 3 | Grade 4 | Grade 3 | Grade 4
Hematology parameters [p less than 0.001 (difference in Grade 3 plus 4 abnormalities between the two treatment groups).]
- Neutropenia* | 13.1 | 3.6 | 20.8 | 4.5
- Thrombocytopenia* | 8.5 | 0.4 | 15.9 | 0.6
- Anemia | 3.3 | 1.1 | 4.1 | 0.2
Biochemistry parameters
- Elevated creatinine | 0 | 0 | 0.4 | 0
- Elevated bilirubin | 0.9 | 0.2 | 0.2 | 0
- Elevated alkaline phosphatase | 0.2 | 0 | 0.8 | 0
- Elevated SGOT (AST)/SGPT (ALT) | 4.7 | 0.5 | 7.1 | 0.4
Abbreviations: CML, chronic myeloid leukemia; IFN, Interferon-alpha; SGOT, serum glutamic-oxaloacetic transaminase is now referred to as aspartate aminotransferase (AST); SGPT, serum glutamic-pyruvic transaminase is now referred to as alanine aminotransferase (ALT).

Table 6: Percent Incidence of Clinically Relevant Grade 3/4 [NCI Common Terminology Criteria for Adverse Events, version 3.0.] Laboratory Abnormalities in the Newly Diagnosed CML Clinical Trial (Imatinib Versus Nilotinib)
 | Imatinib 400 mg once daily | Nilotinib 300 mg twice daily
 | N = 280 | N = 279
 | (%) | (%)
Hematologic parameters
Thrombocytopenia | 9 | 10
Neutropenia | 22 | 12
Anemia | 6 | 4
Biochemistry parameters
Elevated lipase | 4 | 9
Hyperglycemia | < 1 | 7
Hypophosphatemia | 10 | 8
Elevated bilirubin (total) | < 1 | 4
Elevated SGPT (ALT) | 3 | 4
Hyperkalemia | 1 | 2
Hyponatremia | < 1 | 1
Hypokalemia | 2 | < 1
Elevated SGOT (AST) | 1 | 1
Decreased albumin | < 1 | 0
Hypocalcemia | < 1 | < 1
Elevated alkaline phosphatase | < 1 | 0
Elevated creatinine | < 1 | 0
Abbreviations: CML, chronic myeloid leukemia; SGOT, serum glutamic-oxaloacetic transaminase is now referred to as aspartate aminotransferase (AST); SGPT, serum glutamic-pyruvic transaminase is now referred to as alanine aminotransferase (ALT).

Table 7: Laboratory Abnormalities in Other CML Clinical Trials
 | Myeloid blast crisis |  | Accelerated phase |  | Chronic phase, IFN failure
 | (n = 260) |  | (n = 235) |  | (n = 532)
 | 600 mg n = 223 |  | 600 mg n = 158
 | 400 mg n = 37 |  | 400 mg n = 77 |  | 400 mg
 | % |  | % |  | %
CTC Grades [CTC Grades: neutropenia (Grade 3 greater than or equal to 0.5-1.0 x 10^9/L, Grade 4 less than 0.5 x 10^9/L), thrombocytopenia (Grade 3 greater than or equal to 10-50 x 10^9/L, Grade 4 less than 10 x 10^9/L), anemia (hemoglobin greater than or equal to 65-80 g/L, Grade 4 less than 65 g/L), elevated creatinine (Grade 3 greater than 3-6 x upper limit normal range [ULN], Grade 4 greater than 6 x ULN), elevated bilirubin (Grade 3 greater than 3-10 x ULN, Grade 4 greater than 10 x ULN), elevated alkaline phosphatase (Grade 3 greater than 5-20 x ULN, Grade 4 greater than 20 x ULN), elevated SGOT or SGPT (Grade 3 greater than 5-20 x ULN, Grade 4 greater than 20 x ULN).] | Grade 3 | Grade 4 | Grade 3 | Grade 4 | Grade 3 | Grade 4
Hematology parameters
- Neutropenia | 16 | 48 | 23 | 36 | 27 | 9
- Thrombocytopenia | 30 | 33 | 31 | 13 | 21 | < 1
- Anemia | 42 | 11 | 34 | 7 | 6 | 1
Biochemistry parameters
- Elevated creatinine | 1.5 | 0 | 1.3 | 0 | 0.2 | 0
- Elevated bilirubin | 3.8 | 0 | 2.1 | 0 | 0.6 | 0
- Elevated alkaline phosphatase | 4.6 | 0 | 5.5 | 0.4 | 0.2 | 0
- Elevated SGOT (AST) | 1.9 | 0 | 3.0 | 0 | 2.3 | 0
- Elevated SGPT (ALT) | 2.3 | 0.4 | 4.3 | 0 | 2.1 | 0
Abbreviations: CML, chronic myeloid leukemia; CTC, common terminology criteria; IFN, Interferon-alpha; SGOT, serum glutamic-oxaloacetic transaminase is now referred to as aspartate aminotransferase (AST); SGPT, serum glutamic-pyruvic transaminase is now referred to as alanine aminotransferase (ALT).

Hepatotoxicity

Severe elevation of transaminases or bilirubin occurred in approximately 5% of CML patients (see Tables 6 and 7) and were usually managed with dose reduction or interruption (the median duration of these episodes was approximately 1 week). Treatment was discontinued permanently because of liver laboratory abnormalities in less than 1.0% of CML patients. One patient, who was taking acetaminophen regularly for fever, died of acute liver failure. In the Phase 2 GIST trial, Grade 3 or 4 SGPT (ALT) elevations were observed in 6.8% of patients and Grade 3 or 4 SGOT (AST) elevations were observed in 4.8% of patients. Bilirubin elevation was observed in 2.7% of patients.

Adverse Reactions in Pediatric Population

Single-Agent Therapy

The overall safety profile of pediatric patients treated with imatinib in 93 children studied was similar to that found in studies with adult patients, except that musculoskeletal pain was less frequent (20.5%) and peripheral edema was not reported. Nausea and vomiting were the most commonly reported individual adverse reactions with an incidence similar to that seen in adult patients. Most patients experienced adverse reactions at some time during the study. The incidence of Grade 3/4 events across all types of adverse reactions was 75%; the events with the highest Grade 3/4 incidence in CML pediatric patients were mainly related to myelosuppression.

In Combination with Multi-Agent Chemotherapy

Pediatric and young adult patients with very high risk ALL, defined as those with an expected 5 year event-free survival (EFS) less than 45%, were enrolled after induction therapy on a multicenter, non-randomized cooperative group pilot protocol. The study population included patients with a median age of 10 years (1 to 21 years), 61% of whom were male, 75% were White, 7% were Black, and 6% were Asian/Pacific Islander. Patients with Ph+ ALL (n = 92) were assigned to receive imatinib and treated in 5 successive cohorts. Imatinib exposure was systematically increased in successive cohorts by earlier introduction and more prolonged duration.

The safety of imatinib given in combination with intensive chemotherapy was evaluated by comparing the incidence of Grade 3 and 4 adverse events, neutropenia (less than 750/mcL) and thrombocytopenia (less than 75,000/mcL) in the 92 patients with Ph+ ALL compared to 65 patients with Ph- ALL enrolled on the trial who did not receive imatinib. The safety was also evaluated comparing the incidence of adverse events in cycles of therapy administered with or without imatinib. The protocol included up to 18 cycles of therapy. Patients were exposed to a cumulative total of 1425 cycles of therapy, 778 with imatinib, and 647 without imatinib. The adverse events that were reported with a 5% or greater incidence in patients with Ph+ ALL compared to Ph- ALL or with a 1% or greater incidence in cycles of therapy that included imatinib are presented in Table 8.

Table 8: Adverse Reactions Reported More Frequently in Patients Treated With Study Drug (Greater Than 5%) or in Cycles With Study Drug (Greater Than 1%)
Adverse event | Per patient incidence Ph+ ALL with Imatinib N = 92 n (%) | Per patient incidence Ph- ALL no Imatinib N = 65 n (%) | Per patient per cycle incidence with Imatinib [Defined as the frequency of adverse events (AEs) per patient per treatment cycles that included imatinib (includes patients with Ph+ ALL that received cycles with imatinib).] N = 778 n (%) | Per patient per cycle incidence no Imatinib [Defined as the frequency of AEs per patient per treatment cycles that did not include imatinib (includes patients with Ph+ ALL that received cycles without imatinib as well as all patients with Ph- ALL who did not receive imatinib in any treatment cycle).] N = 647 n (%)
Grade 3 and 4 adverse events
Nausea and/or vomiting | 15 (16) | 6 (9) | 28 (4) | 8 (1)
Hypokalemia | 31 (34) | 16 (25) | 72 (9) | 32 (5)
Pneumonitis | 7 (8) | 1 (1) | 7 (1) | 1 (< 1)
Pleural effusion | 6 (7) | 0 | 6 (1) | 0
Abdominal pain | 8 (9) | 2 (3) | 9 (1) | 3 (< 1)
Anorexia | 10 (11) | 3 (5) | 19 (2) | 4 (1)
Hemorrhage | 11 (12) | 4 (6) | 17 (2) | 8 (1)
Hypoxia | 8 (9) | 2 (3) | 12 (2) | 2 (< 1)
Myalgia | 5 (5) | 0 | 4 (1) | 1 (< 1)
Stomatitis | 15 (16) | 8 (12) | 22 (3) | 14 (2)
Diarrhea | 8 (9) | 3 (5) | 12 (2) | 3 (< 1)
Rash/Skin disorder | 4 (4) | 0 | 5 (1) | 0
Infection | 49 (53) | 32 (49) | 131 (17) | 92 (14)
Hepatic (transaminase and/or bilirubin) | 52 (57) | 38 (58) | 172 (22) | 113 (17)
Hypotension | 10 (11) | 5 (8) | 16 (2) | 6 (1)
Myelosuppression
Neutropenia (< 750/mcL) | 92 (100) | 63 (97) | 556 (71) | 218 (34)
Thrombocytopenia (< 75,000/mcL) | 90 (92) | 63 (97) | 431 (55) | 329 (51)
Abbreviations: Ph+ ALL, Philadelphia chromosome positive acute lymphoblastic leukemia; Ph- ALL, Philadelphia chromosome negative acute lymphoblastic leukemia.

Adverse Reactions in Other Subpopulations

In older patients (greater than or equal to 65 years old), with the exception of edema, where it was more frequent, there was no evidence of an increase in the incidence or severity of adverse reactions. In women there was an increase in the frequency of neutropenia, as well as Grade 1/2 superficial edema, headache, nausea, rigors, vomiting, rash, and fatigue. No differences were seen that were related to race but the subsets were too small for proper evaluation.

Acute Lymphoblastic Leukemia

The adverse reactions were similar for Ph+ ALL as for Ph+ CML. The most frequently reported drug-related adverse reactions reported in the Ph+ ALL studies were mild nausea and vomiting, diarrhea, myalgia, muscle cramps, and rash. Superficial edema was a common finding in all studies and were described primarily as periorbital or lower limb edemas. These edemas were reported as Grade 3/4 events in 6.3% of the patients and may be managed with diuretics, other supportive measures, or in some patients by reducing the dose of imatinib.

Myelodysplastic/Myeloproliferative Diseases

Adverse reactions, regardless of relationship to study drug, that were reported in at least 10% of the patients treated with imatinib for MDS/MPD in the Phase 2 study, are shown in Table 9.

Table 9: Adverse Reactions Regardless of Relationship to Study Drug Reported (More Than One Patient) in MPD Patients in the Phase 2 Study (Greater Than or Equal to 10% All Patients) All Grades
 | N = 7
Preferred term | n (%)
Nausea | 4 (57.1)
Diarrhea | 3 (42.9)
Anemia | 2 (28.6)
Fatigue | 2 (28.6)
Muscle cramp | 3 (42.9)
Arthralgia | 2 (28.6)
Periorbital edema | 2 (28.6)
Abbreviation: MPD, myeloproliferative disease.

Aggressive Systemic Mastocytosis

All aggressive systemic mastocytosis (ASM) patients experienced at least one adverse reaction at some time. The most frequently reported adverse reactions were diarrhea, nausea, ascites, muscle cramps, dyspnea, fatigue, peripheral edema, anemia, pruritus, rash, and lower respiratory tract infection. None of the 5 patients in the Phase 2 study with ASM discontinued imatinib due to drug-related adverse reactions or abnormal laboratory values.

Hypereosinophilic Syndrome and Chronic Eosinophilic Leukemia

The safety profile in the HES/CEL patient population does not appear to be different from the safety profile of imatinib observed in other hematologic malignancy populations, such as Ph+ CML. All patients experienced at least one adverse reaction, the most common being GI, cutaneous and musculoskeletal disorders. Hematological abnormalities were also frequent, with instances of CTC Grade 3 leukopenia, neutropenia, lymphopenia, and anemia.

Dermatofibrosarcoma Protuberans

Adverse reactions, regardless of relationship to study drug, that were reported in at least 10% of the 12 patients treated with imatinib for DFSP in the Phase 2 study are shown in Table 10.

Table 10: Adverse Reactions Regardless of Relationship to Study Drug Reported in DFSP Patients in the Phase 2 Study (Greater Than or Equal to 10% All Patients) All Grades
 | N = 12
Preferred term | n (%)
Nausea | 5 (41.7)
Diarrhea | 3 (25.0)
Vomiting | 3 (25.0)
Periorbital edema | 4 (33.3)
Face edema | 2 (16.7)
Rash | 3 (25.0)
Fatigue | 5 (41.7)
Peripheral edema | 4 (33.3)
Pyrexia | 2 (16.7)
Eye edema | 4 (33.3)
Lacrimation increased | 3 (25.0)
Dyspnea exertional | 2 (16.7)
Anemia | 3 (25.0)
Rhinitis | 2 (16.7)
Anorexia | 2 (16.7)
Abbreviation: DFSP, dermatofibrosarcoma protuberans.

Clinically relevant or severe laboratory abnormalities in the 12 patients treated with imatinib for DFSP in the Phase 2 study are presented in Table 11.

Table 11: Laboratory Abnormalities Reported in DFSP Patients in the Phase 2 Study
 | N = 12
CTC Grades [CTC Grades: neutropenia (Grade 3 greater than or equal to 0.5-1.0 x 10^9/L, Grade 4 less than 0.5 x 10^9/L), thrombocytopenia (Grade 3 greater than or equal to 10-50 x 10^9/L, Grade 4 less than 10 x 10^9/L), anemia (Grade 3 greater than or equal to 65-80 g/L, Grade 4 less than 65 g/L), elevated creatinine (Grade 3 greater than 3-6 x upper limit normal range [ULN], Grade 4 greater than 6 x ULN).] | Grade 3 % | Grade 4 %
Hematology parameters
- Anemia | 17 | 0
- Thrombocytopenia | 17 | 0
- Neutropenia | 0 | 8
Biochemistry parameters
- Elevated creatinine | 0 | 8
Abbreviation: CTC, common terminology criteria.

Gastrointestinal Stromal Tumors

Unresectable and/or Malignant Metastatic GIST

In the Phase 3 trials, the majority of imatinib-treated patients experienced adverse reactions at some time. The most frequently reported adverse reactions were edema, fatigue, nausea, abdominal pain, diarrhea, rash, vomiting, myalgia, anemia, and anorexia. Drug was discontinued for adverse reactions in a total of 89 patients (5.4%). Superficial edema, most frequently periorbital or lower extremity edema was managed with diuretics, other supportive measures, or by reducing the dose of imatinib [see Dosage and Administration (2.13)]. Severe (CTC Grade 3/4) edema was observed in 182 patients (11.1%).

Adverse reactions, regardless of relationship to study drug, that were reported in at least 10% of the patients treated with imatinib are shown in Table 12.

Overall the incidence of all grades of adverse reactions and the incidence of severe adverse reactions (CTC Grade 3 and above) were similar between the two treatment arms except for edema, which was reported more frequently in the 800 mg group.

Table 12: Number (%) of Patients With Adverse Reactions Regardless of Relationship to Study Drug Where Frequency is Greater Than or Equal to 10% in any One Group (Full Analysis Set) in the Phase 3 Unresectable and/or Malignant Metastatic GIST Clinical Trials
 | Imatinib 400 mg N = 818 |  | Imatinib 800 mg N = 822
 | All Grades | Grades 3/4/5 | All Grades | Grades 3/4/5
Reported or specified term | % | % | % | %
Edema | 76.7 | 9.0 | 86.1 | 13.1
Fatigue/lethargy, malaise, asthenia | 69.3 | 11.7 | 74.9 | 12.2
Nausea | 58.1 | 9.0 | 64.5 | 7.8
Abdominal pain/cramping | 57.2 | 13.8 | 55.2 | 11.8
Diarrhea | 56.2 | 8.1 | 58.2 | 8.6
Rash/desquamation | 38.1 | 7.6 | 49.8 | 8.9
Vomiting | 37.4 | 9.2 | 40.6 | 7.5
Myalgia | 32.2 | 5.6 | 30.2 | 3.8
Anemia | 32.0 | 4.9 | 34.8 | 6.4
Anorexia | 31.1 | 6.6 | 35.8 | 4.7
Other GI toxicity | 25.2 | 8.1 | 28.1 | 6.6
Headache | 22.0 | 5.7 | 19.7 | 3.6
Other pain (excluding tumor related pain) | 20.4 | 5.9 | 20.8 | 5.0
Other dermatology/skin toxicity | 17.6 | 5.9 | 20.1 | 5.7
Leukopenia | 17.0 | 0.7 | 19.6 | 1.6
Other constitutional symptoms | 16.7 | 6.4 | 15.2 | 4.4
Cough | 16.1 | 4.5 | 14.5 | 3.2
Infection (without neutropenia) | 15.5 | 6.6 | 16.5 | 5.6
Pruritus | 15.4 | 5.4 | 18.9 | 4.3
Other neurological toxicity | 15.0 | 6.4 | 15.2 | 4.9
Constipation | 14.8 | 5.1 | 14.4 | 4.1
Other renal/genitourinary toxicity | 14.2 | 6.5 | 13.6 | 5.2
Arthralgia (joint pain) | 13.6 | 4.8 | 12.3 | 3.0
Dyspnea (shortness of breath) | 13.6 | 6.8 | 14.2 | 5.6
Fever in absence of neutropenia (ANC < 1.0 x 10^9/L) | 13.2 | 4.9 | 12.9 | 3.4
Sweating | 12.7 | 4.6 | 8.5 | 2.8
Other hemorrhage | 12.3 | 6.7 | 13.3 | 6.1
Weight gain | 12.0 | 1.0 | 10.6 | 0.6
Alopecia | 11.9 | 4.3 | 14.8 | 3.2
Dyspepsia/heartburn | 11.5 | 0.6 | 10.9 | 0.5
Neutropenia/granulocytopenia | 11.5 | 3.1 | 16.1 | 4.1
Rigors/chills | 11.0 | 4.6 | 10.2 | 3.0
Dizziness/lightheadedness | 11.0 | 4.8 | 10.0 | 2.8
Creatinine increase | 10.8 | 0.4 | 10.1 | 0.6
Flatulence | 10.0 | 0.2 | 10.1 | 0.1
Stomatitis/pharyngitis (oral/pharyngeal mucositis) | 9.2 | 5.4 | 10.0 | 4.3
Lymphopenia | 6.0 | 0.7 | 10.1 | 1.9

Abbreviations: ANC, absolute neutrophil count; GI, gastrointestinal; GIST, gastrointestinal stromal tumors.

Clinically relevant or severe abnormalities of routine hematologic or biochemistry laboratory values were not reported or evaluated in the Phase 3 GIST trials. Severe abnormal laboratory values reported in the Phase 2 GIST trial are presented in Table 13.

Table 13: Laboratory Abnormalities in the Phase 2 Unresectable and/or Malignant Metastatic GIST Trial
 | 400 mg (n = 73) % |  | 600 mg (n = 74) %
CTC Grades [CTC Grades: neutropenia (Grade 3 greater than or equal to 0.5-1.0 x 10^9/L, Grade 4 less than 0.5 x 10^9/L), thrombocytopenia (Grade 3 greater than or equal to 10-50 x 10^9/L, Grade 4 less than 10 x 10^9/L), anemia (Grade 3 greater than or equal to 65-80 g/L, Grade 4 less than 65 g/L), elevated creatinine (Grade 3 greater than 3-6 x upper limit normal range [ULN], Grade 4 greater than 6 x ULN), elevated bilirubin (Grade 3 greater than 3-10 x ULN, Grade 4 greater than 10 x ULN), elevated alkaline phosphatase, SGOT or SGPT (Grade 3 greater than 5-20 x ULN, Grade 4 greater than 20 x ULN), albumin (Grade 3 less than 20 g/L).] | Grade 3 | Grade 4 | Grade 3 | Grade 4
Hematology parameters
- Anemia | 3 | 0 | 8 | 1
- Thrombocytopenia | 0 | 0 | 1 | 0
- Neutropenia | 7 | 3 | 8 | 3
Biochemistry parameters
- Elevated creatinine | 0 | 0 | 3 | 0
- Reduced albumin | 3 | 0 | 4 | 0
- Elevated bilirubin | 1 | 0 | 1 | 3
- Elevated alkaline phosphatase | 0 | 0 | 3 | 0
- Elevated SGOT (AST) | 4 | 0 | 3 | 3
- Elevated SGPT (ALT) | 6 | 0 | 7 | 1
Abbreviations: CTC, common terminology criteria; GIST, gastrointestinal stromal tumors; SGOT, serum glutamic-oxaloacetic transaminase is now referred to as aspartate aminotransferase (AST); SGPT, serum glutamic-pyruvic transaminase is now referred to as alanine aminotransferase (ALT).

Adjuvant Treatment of GIST

In Study 1, the majority of both imatinib and placebo-treated patients experienced at least one adverse reaction at some time. The most frequently reported adverse reactions were similar to those reported in other clinical studies in other patient populations and include diarrhea, fatigue, nausea, edema, decreased hemoglobin, rash, vomiting, and abdominal pain. No new adverse reactions were reported in the adjuvant GIST-treatment setting that had not been previously reported in other patient populations, including patients with unresectable and/or malignant metastatic GIST. Drug was discontinued for adverse reactions in 57 patients (17%) and 11 patients (3%) of the imatinib and placebo-treated patients, respectively. Edema, GI disturbances (nausea, vomiting, abdominal distention, and diarrhea), fatigue, low hemoglobin, and rash were the most frequently reported adverse reactions at the time of discontinuation.

In Study 2, discontinuation of therapy due to adverse reactions occurred in 15 patients (8%) and 27 patients (14%) of the imatinib 12-month, and 36-month treatment arms, respectively. As in previous trials the most common adverse reactions were diarrhea, fatigue, nausea, edema, decreased hemoglobin, rash, vomiting, and abdominal pain.

Adverse reactions, regardless of relationship to study drug, that were reported in at least 5% of the patients treated with imatinib are shown in Table 14 (Study 1) and Table 15 (Study 2). There were no deaths attributable to imatinib treatment in either trial.

Table 14: Adverse Reactions Regardless of Relationship to Study Drug Reported in Study 1 (Greater Than or Equal to 5% of Imatinib-Treated Patients) [All adverse reactions occurring in greater than or equal to 5% of patients are listed regardless of suspected relationship to treatment. A patient with multiple occurrences of an adverse reaction is counted only once in the adverse reaction category.]
 | All CTC Grades |  | CTC Grade 3 [NCI Common Terminology Criteria for Adverse Events, version 3.0.] and Above
 | Imatinib | Placebo | Imatinib | Placebo
 | (n = 337) | (n = 345) | (n = 337) | (n = 345)
Preferred term | % | % | % | %
Diarrhea | 59.3 | 29.3 | 3.0 | 1.4
Fatigue | 57.0 | 40.9 | 2.1 | 1.2
Nausea | 53.1 | 27.8 | 2.4 | 1.2
Periorbital edema | 47.2 | 14.5 | 1.2 | 0
Hemoglobin decreased | 46.9 | 27.0 | 0.6 | 0
Peripheral edema | 26.7 | 14.8 | 0.3 | 0
Rash (Exfoliative) | 26.1 | 12.8 | 2.7 | 0
Vomiting | 25.5 | 13.9 | 2.4 | 0.6
Abdominal pain | 21.1 | 22.3 | 3.0 | 1.4
Headache | 19.3 | 20.3 | 0.6 | 0
Dyspepsia | 17.2 | 13.0 | 0.9 | 0
Anorexia | 16.9 | 8.7 | 0.3 | 0
Weight increased | 16.9 | 11.6 | 0.3 | 0
Liver enzymes (ALT) increased | 16.6 | 13.0 | 2.7 | 0
Muscle spasms | 16.3 | 3.3 | 0 | 0
Neutrophil count decreased | 16.0 | 6.1 | 3.3 | 0.9
Arthralgia | 15.1 | 14.5 | 0 | 0.3
White blood cell count decreased | 14.5 | 4.3 | 0.6 | 0.3
Constipation | 12.8 | 17.7 | 0 | 0.3
Dizziness | 12.5 | 10.7 | 0 | 0.3
Liver enzymes (AST) increased | 12.2 | 7.5 | 2.1 | 0
Myalgia | 12.2 | 11.6 | 0 | 0.3
Blood creatinine increased | 11.6 | 5.8 | 0 | 0.3
Cough | 11.0 | 11.3 | 0 | 0
Pruritus | 11.0 | 7.8 | 0.9 | 0
Weight decreased | 10.1 | 5.2 | 0 | 0
Hyperglycemia | 9.8 | 11.3 | 0.6 | 1.7
Insomnia | 9.8 | 7.2 | 0.9 | 0
Lacrimation increased | 9.8 | 3.8 | 0 | 0
Alopecia | 9.5 | 6.7 | 0 | 0
Flatulence | 8.9 | 9.6 | 0 | 0
Rash | 8.9 | 5.2 | 0.9 | 0
Abdominal distension | 7.4 | 6.4 | 0.3 | 0.3
Back pain | 7.4 | 8.1 | 0.6 | 0
Pain in extremity | 7.4 | 7.2 | 0.3 | 0
Hypokalemia | 7.1 | 2.0 | 0.9 | 0.6
Depression | 6.8 | 6.4 | 0.9 | 0.6
Facial edema | 6.8 | 1.2 | 0.3 | 0
Blood alkaline phosphatase increased | 6.5 | 7.5 | 0 | 0
Dry skin | 6.5 | 5.2 | 0 | 0
Dysgeusia | 6.5 | 2.9 | 0 | 0
Abdominal pain upper | 6.2 | 6.4 | 0.3 | 0
Neuropathy peripheral | 5.9 | 6.4 | 0 | 0
Hypocalcemia | 5.6 | 1.7 | 0.3 | 0
Leukopenia | 5.0 | 2.6 | 0.3 | 0
Platelet count decreased | 5.0 | 3.5 | 0 | 0
Stomatitis | 5.0 | 1.7 | 0.6 | 0
Upper respiratory tract infection | 5.0 | 3.5 | 0 | 0
Vision blurred | 5.0 | 2.3 | 0 | 0
Abbreviations: CTC, common terminology criteria; GIST, gastrointestinal stromal tumors; SGOT, serum glutamic-oxaloacetic transaminase is now referred to as aspartate aminotransferase (AST); SGPT, serum glutamic-pyruvic transaminase is now referred to as alanine aminotransferase (ALT).

Table 15: Adverse Reactions Regardless of Relationship to Study Drug by Preferred Term All Grades and 3/4 Grades (Greater Than or Equal to 5% of Imatinib-Treated Patients) Study 2 [All adverse reactions occurring in greater than or equal to 5% of patients are listed regardless of suspected relationship to treatment. A patient with multiple occurrences of an adverse reaction is counted only once in the adverse reaction category.]
Preferred term | All CTC Grades |  | CTC Grades 3 and above
 | Imatinib 12 Months | Imatinib 36 Months | Imatinib 12 Months | Imatinib 36 Months
 | (N = 194) | (N = 198) | (N = 194) | (N = 198)
 | % | % | % | %
Patients with at least one AE | 99.0 | 100.0 | 20.1 | 32.8
Hemoglobin decreased | 72.2 | 80.3 | 0.5 | 0.5
Periorbital edema | 59.3 | 74.2 | 0.5 | 1.0
Blood lactate dehydrogenase increased | 43.3 | 60.1 | 0 | 0
Diarrhea | 43.8 | 54.0 | 0.5 | 2.0
Nausea | 44.8 | 51.0 | 1.5 | 0.5
Muscle spasms | 30.9 | 49.0 | 0.5 | 1.0
Fatigue | 48.5 | 48.5 | 1.0 | 0.5
White blood cell count decreased | 34.5 | 47.0 | 2.1 | 3.0
Pain | 25.8 | 45.5 | 1.0 | 3.0
Blood creatinine increased | 30.4 | 44.4 | 0 | 0
Peripheral edema | 33.0 | 40.9 | 0.5 | 1.0
Dermatitis | 29.4 | 38.9 | 2.1 | 1.5
Aspartate aminotransferase increased | 30.9 | 37.9 | 1.5 | 3.0
Alanine aminotransferase increased | 28.9 | 34.3 | 2.1 | 3.0
Neutrophil count decreased | 24.2 | 33.3 | 4.6 | 5.1
Hypoproteinemia | 23.7 | 31.8 | 0 | 0
Infection | 13.9 | 27.8 | 1.5 | 2.5
Weight increased | 13.4 | 26.8 | 0 | 0.5
Pruritus | 12.9 | 25.8 | 0 | 0
Flatulence | 19.1 | 24.7 | 1.0 | 0.5
Vomiting | 10.8 | 22.2 | 0.5 | 1.0
Dyspepsia | 17.5 | 21.7 | 0.5 | 1.0
Hypoalbuminemia | 11.9 | 21.2 | 0 | 0
Edema | 10.8 | 19.7 | 0 | 0.5
Abdominal distension | 11.9 | 19.2 | 0.5 | 0
Headache | 8.2 | 18.2 | 0 | 0
Lacrimation increased | 18.0 | 17.7 | 0 | 0
Arthralgia | 8.8 | 17.2 | 0 | 1.0
Blood alkaline phosphatase increased | 10.8 | 16.7 | 0 | 0.5
Dyspnea | 6.2 | 16.2 | 0.5 | 1.5
Myalgia | 9.3 | 15.2 | 0 | 1.0
Platelet count decreased | 11.3 | 14.1 | 0 | 0
Blood bilirubin increased | 11.3 | 13.1 | 0 | 0
Dysgeusia | 9.3 | 12.6 | 0 | 0
Paresthesia | 5.2 | 12.1 | 0 | 0.5
Vision blurred | 10.8 | 11.1 | 1.0 | 0.5
Alopecia | 11.3 | 10.6 | 0 | 0
Decreased appetite | 9.8 | 10.1 | 0 | 0
Constipation | 8.8 | 9.6 | 0 | 0
Pyrexia | 6.2 | 9.6 | 0 | 0
Depression | 3.1 | 8.1 | 0 | 0
Abdominal pain | 2.6 | 7.6 | 0 | 0
Conjunctivitis | 5.2 | 7.6 | 0 | 0
Photosensitivity reaction | 3.6 | 7.1 | 0 | 0
Dizziness | 4.6 | 6.6 | 0.5 | 0
Hemorrhage | 3.1 | 6.6 | 0
Dry skin | 6.7 | 6.1 | 0.5
Nasopharyngitis | 1.0 | 6.1 | 0 | 0.5
Palpitations | 5.2 | 5.1 | 0 | 0
Abbreviations: AE, adverse event; CTC, common terminology criteria.

Adverse Reactions from Multiple Clinical Trials

Cardiac Disorders:

Estimated 1%-10%: palpitations, pericardial effusion

Estimated 0.1%-1%: congestive cardiac failure, tachycardia, pulmonary edema

Estimated 0.01%-0.1%: arrhythmia, atrial fibrillation, cardiac arrest, myocardial infarction, angina pectoris

Vascular Disorders:

Estimated 1%-10%: flushing, hemorrhage

Estimated 0.1%-1%: hypertension, hypotension, peripheral coldness, Raynaud’s phenomenon, hematoma, subdural hematoma

Investigations:

Estimated 1%-10%: blood creatine phosphokinase (CPK) increased, blood amylase increased Estimated 0.1%-1%: blood lactate dehydrogenase (LDH) increased

Skin and Subcutaneous Tissue Disorders:

Estimated 1%-10%: dry skin, alopecia, face edema, erythema, photosensitivity reaction, nail disorder, purpura

Estimated 0.1%-1%: exfoliative dermatitis, bullous eruption, psoriasis, rash pustular, contusion, sweating increased, urticaria, ecchymosis, increased tendency to bruise, hypotrichosis, skin hypopigmentation, skin hyperpigmentation, onychoclasis, folliculitis, petechiae, erythema multiforme, panniculitis (including erythema nodosum)

Estimated 0.01%-0.1%: vesicular rash, Stevens-Johnson syndrome, acute generalized exanthematous pustulosis, acute febrile neutrophilic dermatosis (Sweet’s syndrome), nail discoloration, angioneurotic edema, leucocytoclastic vasculitis

Gastrointestinal Disorders:

Estimated 1%-10%: abdominal distention, gastroesophageal reflux, dry mouth, gastritis

Estimated 0.1%-1%: gastric ulcer, stomatitis, mouth ulceration, eructation, melena, esophagitis, ascites, hematemesis, chelitis, dysphagia, pancreatitis

Estimated 0.01%-0.1%: colitis, ileus, inflammatory bowel disease

General Disorders and Administration-Site Conditions:

Estimated 1%-10%: weakness, anasarca, chills Estimated 0.1%-1%: malaise

Blood and Lymphatic System Disorders:

Estimated 1%-10%: pancytopenia, febrile neutropenia, lymphopenia, eosinophilia Estimated 0.1%-1%: thrombocythemia, bone marrow depression, lymphadenopathy Estimated 0.01%-0.1%: hemolytic anemia, aplastic anemia

Hepatobiliary Disorders:

Estimated 0.1%-1%: hepatitis, jaundice

Estimated 0.01%-0.1%: hepatic failure and hepatic necrosis^1

Immune System Disorders:

Estimated 0.01%-0.1%: angioedema

Infections and Infestations:

Estimated 0.1%-1%: sepsis, herpes simplex, herpes zoster, cellulitis, urinary tract infection, gastroenteritis Estimated 0.01%-0.1%: fungal infection

Metabolism and Nutrition Disorders:

Estimated 1%-10%: weight decreased, decreased appetite

Estimated 0.1%-1%: dehydration, gout, increased appetite, hyperuricemia, hypercalcemia, hyperglycemia, hyponatremia, hyperkalemia, hypomagnesemia

Musculoskeletal and Connective Tissue Disorders:

Estimated 1%-10%: joint swelling

Estimated 0.1%-1%: joint and muscle stiffness, muscular weakness, arthritis

Nervous System/Psychiatric Disorders:

Estimated 1%-10%: paresthesia, hypesthesia

Estimated 0.1%-1%: syncope, peripheral neuropathy, somnolence, migraine, memory impairment, libido decreased, sciatica, restless leg syndrome, tremor

Estimated 0.01%-0.1%: increased intracranial pressure^1, confusional state, convulsions, optic neuritis

Renal and Urinary Disorders:

Estimated 0.1%-1%: renal failure acute, urinary frequency increased, hematuria, renal pain

Reproductive System and Breast Disorders:

Estimated 0.1%-1%: breast enlargement, menorrhagia, sexual dysfunction, gynecomastia, erectile dysfunction, menstruation irregular, nipple pain, scrotal edema

Respiratory, Thoracic and Mediastinal Disorders:

Estimated 1%-10%: epistaxis Estimated 0.1%-1%: pleural effusion

Estimated 0.01%-0.1%: interstitial pneumonitis, pulmonary fibrosis, pleuritic pain, pulmonary hypertension, pulmonary hemorrhage

Endocrine Disorders:

Estimated 0.1%-1%: hypothyroidism, hyperthyroidism

Eye, Ear, and Labyrinth Disorders:

Estimated 1%-10%: conjunctivitis, vision blurred, orbital edema, conjunctival hemorrhage, dry eye

Estimated 0.1%-1%: vertigo, tinnitus, eye irritation, eye pain, scleral hemorrhage, retinal hemorrhage, blepharitis, macular edema, hearing loss, cataract

Estimated 0.01%-0.1%: papilledema^1, glaucoma

^1Including some fatalities.

6.2 Postmarketing Experience

The following additional adverse reactions have been identified during post approval use of imatinib. Because these reactions are reported voluntarily from a population of uncertain size, it is not always possible to reliably estimate their frequency or establish a causal relationship to drug exposure.

Blood and Lymphatic System Disorders: thrombotic microangiopathy

Cardiac Disorders: pericarditis, cardiac tamponade^1

Eye Disorders: vitreous hemorrhage

Gastrointestinal Disorders: ileus/intestinal obstruction, tumor hemorrhage/tumor necrosis, GI perforation^1 [see Warnings and Precautions (5.6)], diverticulitis, gastric antral vascular ectasia

Infections: hepatitis B virus reactivation^1

Musculoskeletal and Connective Tissue Disorders: osteonecrosis, rhabdomyolysis/myopathy, growth retardation in children, musculoskeletal pain upon treatment discontinuation (including myalgia, pain in extremity, arthralgia, bone pain)

Nervous System Disorders: cerebral edema^1

Reproduction Disorders: hemorrhagic corpus luteum/hemorrhagic ovarian cyst

Respiratory, Thoracic and Mediastinal Disorders: acute respiratory failure^1, interstitial lung disease

Skin and Subcutaneous Tissue Disorders: lichenoid keratosis, lichen planus, toxic epidermal necrolysis, palmar-plantar erythrodysesthesia syndrome, drug rash with eosinophilia and systemic symptoms (DRESS), pseudoporphyria, pemphigus

Vascular Disorders: thrombosis/embolism, anaphylactic shock

^1Including some fatalities.

7 DRUG INTERACTIONS

7.1 Agents Inducing CYP3A Metabolism

Consider alternative therapeutic agents with less enzyme induction potential in patients when rifampin or other strong CYP3A4 inducers are indicated for concomitant use with Imkeldi. The dosage of Imkeldi should be increased if concomitant use with a strong CYP3A4 inducer is required [see Dosage and Administration (2.12)].

Imatinib is a CYP3A substrate. Concomitant use with a strong CYP3A inducer decreases imatinib exposure [see Clinical Pharmacology (12.3)], which may reduce imatinib efficacy.

7.2 Agents Inhibiting CYP3A Metabolism

Caution is recommended when administering Imkeldi with strong CYP3A4 inhibitors. Grapefruit juice should be avoided.

Imatinib is a CYP3A substrate. Concomitant use with a strong CYP3A inhibitor increases imatinib exposure [see Clinical Pharmacology (12.3)], which may increase the risk of Imkeldi adverse reactions.

7.3 Interactions With Drugs Metabolized by CYP3A4

Use caution when administering Imkeldi with CYP3A4 substrates where minimal concentration changes may lead to serious adverse reactions. Because warfarin is metabolized by both CYP2C9 and CYP3A4, use other anti-coagulants instead of warfarin in patients receiving Imkeldi who require anticoagulation.

Imatinib is a CYP3A inhibitor. Imatinib increases exposure of CYP3A substrates [see Clinical Pharmacology (12.3)], which may increase the risk of adverse reactions related to these substrates.

7.4 Interactions With Drugs Metabolized by CYP2D6

Use caution when administering Imkeldi with CYP2D6 substrates where minimal concentration changes may lead to serious adverse reactions.

Imatinib is a CYP2D6 inhibitor. Imatinib increases exposure of CYP2D6 substrates [see Clinical Pharmacology (12.3)], which may increase the risk of adverse reactions related to these substrates.

8 USE IN SPECIFIC POPULATIONS

8.1 Pregnancy

Risk Summary

Imkeldi can cause fetal harm when administered to a pregnant woman based on human and animal data. There are no clinical studies regarding use of Imkeldi in pregnant women. There have been postmarket reports of spontaneous abortions and congenital anomalies from women who have been exposed to imatinib during pregnancy. Reproductive studies in rats have demonstrated that imatinib mesylate induced teratogenicity and increased incidence of congenital abnormalities following prenatal exposure to imatinib mesylate at doses equal to the highest recommended human dose of 800 mg/day based on BSA. Advise pregnant women of the potential risk to a fetus.

The background risk of major birth defects and miscarriage for the indicated population is not known; however, in the U.S. general population, the estimated background risk of major birth defects of clinically recognized pregnancies is 2% to 4% and of miscarriage is 15% to 20%.

Data

Animal Data

In embryo-fetal development studies in rats and rabbits, pregnant animals received oral doses of imatinib mesylate up to 100 mg/kg/day and 60 mg/kg/day, respectively, during the period of organogenesis.

In rats, imatinib mesylate was teratogenic at 100 mg/kg/day (approximately equal to the maximum human dose of 800 mg/day based on BSA), the number of fetuses with encephalocele and exencephaly was higher than historical control values and these findings were associated with missing or underdeveloped cranial bones. Lower mean fetal body weights were associated with retarded skeletal ossifications.

In rabbits, at doses 1.5 times higher than the maximum human dose of 800 mg/day based on BSA, no effects on the reproductive parameters with respect to implantation sites, number of live fetuses, sex ratio or fetal weight were observed. The examinations of the fetuses did not reveal any drug related morphological changes.

In a pre- and postnatal development study in rats, pregnant rats received oral doses of imatinib mesylate during gestation (organogenesis) and lactation up to 45 mg/kg/day. Five animals developed a red vaginal discharge in the 45 mg/kg/day group on Days 14 or 15 of gestation, the significance of which is unknown since all females produced viable litters and none had increased post-implantation loss. Other maternal effects noted only at the dose of 45 mg/kg/day (approximately one-half the maximum human dose of 800 mg/day based on BSA) included an increased number of stillborn pups and pups dying between postpartum Days 0 and 4. In the F1 offspring at this same dose level, mean body weights were reduced from birth until terminal sacrifice and the number of litters achieving criterion for preputial separation was slightly decreased. There were no other significant effects in developmental parameters or behavioral testing. F1 fertility was not affected but reproductive effects were noted at 45 mg/kg/day, including an increased number of resorptions and a decreased number of viable fetuses. The no-observed-effect level (NOEL) for both maternal animals and the F1 generation was 15 mg/kg/day.

8.2 Lactation

Risk Summary

Imatinib and its active metabolite are excreted into human milk. Because of the potential for serious adverse reactions in breastfed children from Imkeldi, advise a lactating woman not to breastfeed during treatment and for 1 month after the last dose.

Human Data

Based on data from 3 breastfeeding women taking imatinib, the milk:plasma ratio is about 0.5 for imatinib and about 0.9 for the active metabolite. Considering the combined concentration of imatinib and active metabolite, a breastfed child could receive up to 10% of the maternal therapeutic dose based on body weight.

8.3 Females and Males of Reproductive Potential

Based on human postmarketing reports and animal studies, Imkeldi can cause fetal harm [see Use in Specific Populations (8.1)].

Pregnancy Testing

Verify pregnancy status in females with reproductive potential prior to the initiation of treatment with Imkeldi.

Contraception

Females

Advise female patients of reproductive potential to use effective contraception (methods that result in less than 1% pregnancy rates) when using Imkeldi during treatment and for fourteen days after stopping treatment with Imkeldi [see Use in Specific Populations (8.1)].

Infertility

The risk of infertility in females or males of reproductive potential has not been studied in humans. In a rat study, the fertility in males and females was not affected [see Nonclinical Toxicology (13)].

8.4 Pediatric Use

The safety and effectiveness of Imkeldi have been established in pediatric patients with newly diagnosed Ph+ chronic phase CML and Ph+ ALL [see Clinical Studies (14.2, 14.4)]. There are no data in pediatric patients under 1 year of age.

The safety and efficacy of Imkeldi have not been established in pediatric patients for all other indications [see Indications and Usage (1)].

8.5 Geriatric Use

In the CML clinical studies, approximately 20% of patients were older than 65 years. In the study of patients with newly diagnosed CML, 6% of patients were older than 65 years. The frequency of edema was higher in patients older than 65 years as compared to younger patients; no other difference in the safety profile was observed [see Warnings and Precautions (5.1)]. The efficacy of imatinib was similar in older and younger patients.

In the unresectable or metastatic GIST study, 16% of patients were older than 65 years. No obvious differences in the safety or efficacy profile were noted in patients older than 65 years as compared to younger patients, but the small number of patients does not allow a formal analysis.

In the adjuvant GIST study, 221 patients (31%) were older than 65 years. No difference was observed in the safety profile in patients older than 65 years as compared to younger patients, with the exception of a higher frequency of edema. The efficacy of imatinib was similar in patients older than 65 years and younger patients.

8.6 Hepatic Impairment

Reduce the dose by 25% for patients with severe hepatic impairment [see Dosage and Administration (2.12)]. Patients with mild hepatic impairment (total bilirubin ≤ upper limit of normal [ULN] and aspartate aminotransferase [AST] >ULN, or total bilirubin ˃1 to 1.5 times ULN and any value for AST) and moderate hepatic impairment (total bilirubin ˃ 1.5 to 3 times ULN and any value for AST) do not require a dose adjustment.

The effect of hepatic impairment on the pharmacokinetics of both imatinib and its major metabolite, CGP74588, was assessed in 84 patients with cancer with varying degrees of hepatic impairment at imatinib doses ranging from 100 mg to 800 mg. Mild hepatic impairment (total bilirubin ≤ ULN and aspartate aminotransferase [AST] > ULN, or total bilirubin ˃1 to 1.5 times ULN and any value for AST) and moderate hepatic impairment (total bilirubin ˃1.5 to 3 times ULN and any value for AST) do not influence exposure to imatinib and CGP74588. In patients with severe hepatic impairment, (total bilirubin ˃ 3 to 10 times ULN and any value for AST), the imatinib Cmax and area under curve (AUC) increased by 63% and 45% and the CGP74588 Cmax and AUC increased by 56% and 55%, relative to patients with normal hepatic function [see Clinical Pharmacology (12.3)].

8.7 Renal Impairment

Dose reductions are necessary for patients with moderate and severe renal impairment [see Dosage and Administration (2.12)].

The effect of renal impairment on the pharmacokinetics of imatinib was assessed in 59 patients with cancer and varying degrees of renal impairment at single and steady state imatinib doses ranging from 100 to 800 mg/day. The mean exposure to imatinib (dose normalized AUC) in patients with mild (CLcr = 40-59 mL/min) and moderate renal impairment (CLcr = 20-39 mL/min) increased 1.5- to 2-fold compared to patients with normal renal function. There are not sufficient data in patients with severe renal impairment (CLcr = less than 20 mL/min) [see Clinical Pharmacology (12.3)].

10 OVERDOSAGE

Experience with doses greater than 800 mg is limited. Isolated cases of imatinib overdose have been reported. In the event of overdosage, observe the patient and give appropriate supportive treatment.

Adult Overdose

1,200 to 1,600 mg (duration varying between 1 to 10 days): Nausea, vomiting, diarrhea, rash erythema, edema, swelling, fatigue, muscle spasms, thrombocytopenia, pancytopenia, abdominal pain, headache, decreased appetite.

1,800 to 3,200 mg (as high as 3,200 mg daily for 6 days): Weakness, myalgia, increased CPK, increased bilirubin, GI pain.

6,400 mg (single dose): One case in the literature reported one patient who experienced nausea, vomiting, abdominal pain, pyrexia, facial swelling, neutrophil count decreased, increase transaminases.

8 to 10 g (single dose): Vomiting and GI pain have been reported.

A patient with myeloid blast crisis experienced Grade 1 elevations of serum creatinine, Grade 2 ascites and elevated liver transaminase levels, and Grade 3 elevations of bilirubin after inadvertently taking 1,200 mg of imatinib daily for 6 days. Therapy was temporarily interrupted and complete reversal of all abnormalities occurred within 1 week. Treatment was resumed at a dose of 400 mg daily without recurrence of adverse reactions. Another patient developed severe muscle cramps after taking 1,600 mg of imatinib daily for 6 days. Complete resolution of muscle cramps occurred following interruption of therapy and treatment was subsequently resumed. Another patient that was prescribed 400 mg daily, took 800 mg of imatinib on Day 1 and 1,200 mg on Day 2. Therapy was interrupted, no adverse reactions occurred and the patient resumed therapy.

Pediatric Overdose

One 3 year old male exposed to a single dose of 400 mg experienced vomiting, diarrhea, and anorexia; and another 3 year old male exposed to a single dose of 980 mg experienced decreased white blood cell (WBC) count and diarrhea.

11 DESCRIPTION

Imkeldi oral solution contains imatinib mesylate, a kinase inhibitor. Imatinib mesylate is designated chemically as 4-[(4-Methyl-1-piperazinyl)methyl]-N-[4-methyl-3-[[4-(3-pyridinyl)-2- pyrimidinyl]amino]-phenyl]benzamide methanesulfonate and its structural formula is:

The molecular formula is C29H31N7O · CH4SO3 and its molecular weight is 589.7 g/mol. Imatinib mesylate is soluble in aqueous buffers less than or equal to pH 5.5 but is very slightly soluble to insoluble in neutral/alkaline aqueous buffers. In non-aqueous solvents, the drug substance is freely soluble to very slightly soluble in dimethyl sulfoxide, methanol, and ethanol, but is insoluble in n-octanol, acetone, and acetonitrile.

Imatinib oral solution is a clear, yellow to brownish yellow colored solution. Each mL of Imkeldi contains the equivalent of 80 mg imatinib present as 95.57 mg imatinib mesylate. Inactive Ingredients: acesulfame potassium, citric acid monohydrate, glycerine, liquid maltitol, purified water, sodium benzoate, strawberry flavor (artificial flavors, lactic acid, triacetin).

12 CLINICAL PHARMACOLOGY

12.1 Mechanism of Action

Imatinib mesylate is a protein-tyrosine kinase inhibitor that inhibits the BCR-ABL tyrosine kinase, the constitutive abnormal tyrosine kinase created by the Philadelphia chromosome abnormality in CML. Imatinib inhibits proliferation and induces apoptosis in BCR-ABL positive cell lines as well as fresh leukemic cells from Philadelphia chromosome positive chronic myeloid leukemia. Imatinib inhibits colony formation in assays using ex vivo peripheral blood and bone marrow samples from CML patients.

In vivo, imatinib inhibits tumor growth of BCR-ABL transfected murine myeloid cells as well as BCR-ABL positive leukemia lines derived from CML patients in blast crisis.

Imatinib is also an inhibitor of the receptor tyrosine kinases for platelet-derived growth factor (PDGF) and stem cell factor (SCF), c-Kit, and inhibits PDGF- and SCF-mediated cellular events. In vitro, imatinib inhibits proliferation and induces apoptosis in GIST cells, which express an activating c-Kit mutation.

12.2 Pharmacodynamics

Imatinib exposure-response relationships and the time course of pharmacodynamic response are unknown.

12.3 Pharmacokinetics

The pharmacokinetics of imatinib have been evaluated in studies in healthy subjects and in population pharmacokinetic studies in over 900 patients. No clinically significant difference in imatinib pharmacokinetics were observed between CML and GIST patients. Imatinib AUC increases proportionally with increasing doses ranging from 25 mg to 1000 mg (0.06 to 1.25 times the approved recommended dosage of 400 mg). Imatinib accumulation is 1.5- to 2.5- fold at steady state when imatinib is dosed once daily.

Absorption

Imatinib mean absolute bioavailability is 98%. Imatinib is well absorbed after oral administration with maximum concentration (Cmax) achieved within 2-4 hours post-dose.

Distribution

Imatinib and the N-demethylated metabolite (CGP74588) plasma protein binding is approximately 95% in vitro, mostly to albumin and α1-acid glycoprotein.

Elimination

The elimination half-life is approximately 18 hours for imatinib and 40 hours for the N-demethyl derivative metabolite (CGP74588), following oral administration in healthy volunteers.

Typical imatinib clearance in a 50-year-old patient weighing 50 kg is expected to be 8 L/h, while for a 50-year-old patient weighing 100 kg the clearance will increase to 14 L/h. The inter-patient variability of 40% in clearance does not warrant initial dose adjustment based on body weight and/or age but indicates the need for close monitoring for treatment-related toxicity.

Metabolism

CYP3A4 is the major enzyme responsible for metabolism of imatinib. Other cytochrome P450 enzymes, such as CYP1A2, CYP2D6, CYP2C9, and CYP2C19, play a minor role in its metabolism. The main circulating active metabolite in humans is the N-demethylated piperazine derivative (CGP74588), formed predominantly by CYP3A4. It shows in vitro potency similar to the parent imatinib. The plasma AUC for this metabolite is about 15% of the AUC for imatinib.

Excretion

Imatinib elimination is predominately in the feces, mostly as metabolites. Following an oral radio-labeled dose of imatinib, approximately 81% of the dose was eliminated within 7 days, in feces (68% of dose) and urine (13% of dose). Unchanged imatinib accounted for 25% of the dose (5% urine, 20% feces), the remainder being metabolites.

Specific Populations

Hepatic Impairment

The effect of hepatic impairment on the pharmacokinetics of both imatinib and its major metabolite, CGP74588, was assessed in 84 patients with cancer and varying degrees of hepatic impairment at imatinib doses ranging from 100 mg to 800 mg.

Exposure to both imatinib and CGP74588 was comparable between each of the mildly (total bilirubin ≤ upper limit of normal [ULN] and aspartate aminotransferase [AST] > ULN, or total bilirubin ˃1 to 1.5 times ULN) and moderately (total bilirubin ˃ 1.5 to 3 times ULN and any value for AST) hepatically-impaired groups and the normal group.

Patients with severe hepatic impairment (Total bilirubin ˃ 3 to 10 times ULN and any value for AST) tend to have higher exposure to both imatinib and CGP74588 than patients with normal hepatic function. At steady state, the mean Cmax/dose and AUC/dose for imatinib increased by about 63% and 45%, respectively, in patients with severe hepatic impairment compared to patients with normal hepatic function. The mean Cmax/dose and AUC/dose for CGP74588 increased by about 56% and 55%, respectively, in patients with severe hepatic impairment compared to patients with normal hepatic function.

Renal Impairment

The effect of renal impairment on the pharmacokinetics of imatinib was assessed in 59 cancer patients with varying degrees of renal impairment at single and steady state imatinib doses ranging from 100 to 800 mg/day.

The mean exposure to imatinib (AUC/dose) in patients with mild (CLcr = 40-59 mL/min) and moderate (CLcr = 20-39 mL/min) renal impairment increased 1.5- to 2-fold compared to patients with normal renal function. The AUCs did not increase for doses greater than 600 mg in patients with mild renal impairment.

The AUCs did not increase for doses greater than 400 mg in patients with moderate renal impairment. Two patients with severe renal impairment (CLcr = less than 20 mL/min) were dosed with 100 mg/day and their exposures were similar to those seen in patients with normal renal function receiving 400 mg/day.

Pediatric Use

Dosing in a limited number of children at both 260 mg/m^2 and 340 mg/m^2 (0.76 and 1 times the approved recommended dosage) achieved an AUC similar to the 400 mg dose in adults. The comparison of AUC on Day 8 vs Day 1 at 260 mg/m^2 and 340 mg/m^2 dose levels revealed a 1.5- and 2.2-fold drug accumulation, respectively, after repeated once-daily dosing. Mean imatinib AUC did not increase proportionally with increasing dose. Another analysis suggested that exposure of imatinib in pediatric patients receiving 260 mg/m^2 once daily (not exceeding 400 mg once daily) or 340 mg/m^2 once daily (not exceeding 600 mg once daily) were similar to those in adult patients who received imatinib 400 mg or 600 mg once daily.

Imatinib time to Cmax is 2-4 hours in pediatric patients which is similar to adult patients. Apparent oral clearance was also similar to adult values (11.0 L/hr/m^2 in children vs 10.0 L/hr/m^2 in adults), as was the half-life (14.8 hours in children vs 17.1 hours in adults).

Imatinib clearance increases with increasing BSA in pediatric patients with hematological disorders (CML, Ph+ ALL, or other hematological disorders treated with imatinib). After correcting for this BSA effect, other demographics, such as age, body weight, and body mass index did not have clinically significant effects on the exposure of imatinib.

Drug Interactions

Clinical Studies

Agents Inducing CYP3A Metabolism

Imatinib oral-dose clearance increased by 3.8-fold, which significantly (p less than 0.05) decreased mean Cmax and AUC, following pretreatment of healthy volunteers with multiple doses of rifampin followed by a single dose of imatinib.

Similar findings were observed in patients receiving 400 to 1200 mg/day imatinib concomitantly with enzyme-inducing anti-epileptic drugs (EIAED) (e.g., carbamazepine, oxcarbamazepine, phenytoin, fosphenytoin, phenobarbital, and primidone). The mean dose normalized AUC for imatinib in the patients receiving EIAED’s decreased by 73% compared to patients not receiving EIAED.

Concomitant administration of imatinib and St. John’s Wort led to a 30% reduction in the AUC of imatinib.

Agents Inhibiting CYP3A Metabolism

There was a significant increase in imatinib exposure (mean Cmax increased by 26% and mean AUC increased by 40%) in healthy subjects following concomitant use of imatinib with a single dose of ketoconazole (CYP3A4 inhibitor).

Interactions with Drugs Metabolized by CYP3A4

Simvastatin (CYP3A4 substrate) mean Cmax increased 2-fold and AUC 3.5-fold, following concomitant use with imatinib.

Interactions with Drugs Metabolized by CYP2D6

Metoprolol (CYP2D6 substrate) mean Cmax and AUC increased by approximately 23% following concomitant use with imatinib.

Interactions with Acetaminophen

Imatinib inhibits the acetaminophen O-glucuronidate pathway in vitro. No clinically significant differences in the pharmacokinetics of acetaminophen or imatinib were observed when acetaminophen (1,000 mg single dose on Day 8) was used concomitantly with imatinib (400 mg/day for 8 days) in patients with CML. There is no pharmacokinetic or safety data on the concomitant use of imatinib at doses greater than 400 mg/day or the chronic use of concomitant acetaminophen and imatinib.

In vitro Studies

CYP450 Metabolism: Imatinib is a substrate of CYP3A4, CYP1A2, CYP2D6, CYP2C9, and CYP2C19. Imatinib is a competitive inhibitor of CYP2C9, CYP2D6, and CYP3A4/5.

13 NONCLINICAL TOXICOLOGY

13.1 Carcinogenesis, Mutagenesis, Impairment of Fertility

In the 2-year rat carcinogenicity study administration of imatinib at 15, 30, and 60 mg/kg/day resulted in a statistically significant reduction in the longevity of males at 60 mg/kg/day and females at greater than or equal to 30 mg/kg/day. Target organs for neoplastic changes were the kidneys (renal tubule and renal pelvis), urinary bladder, urethra, preputial and clitoral gland, small intestine, parathyroid glands, adrenal glands and non-glandular stomach. Neoplastic lesions were not seen at: 30 mg/kg/day for the kidneys, urinary bladder, urethra, small intestine, parathyroid glands, adrenal glands and non-glandular stomach, and 15 mg/kg/day for the preputial and clitoral gland. The papilloma/carcinoma of the preputial/clitoral gland were noted at 30 and 60 mg/kg/day, representing approximately 0.5 to 4 or 0.3 to 2.4 times the human daily exposure (based on AUC) at 400 mg/day or 800 mg/day, respectively, and 0.4 to 3.0 times the daily exposure in children (based on AUC) at 340 mg/m^2. The renal tubule adenoma/carcinoma, renal pelvis transitional cell neoplasms, the urinary bladder and urethra transitional cell papillomas, the small intestine adenocarcinomas, the parathyroid glands adenomas, the benign and malignant medullary tumors of the adrenal glands and the non-glandular stomach papillomas/carcinomas were noted at 60 mg/kg/day. The relevance of these findings in the rat carcinogenicity study for humans is not known.

Positive genotoxic effects were obtained for imatinib in an in vitro mammalian cell assay (Chinese hamster ovary) for clastogenicity (chromosome aberrations) in the presence of metabolic activation. Two intermediates of the manufacturing process, which are also present in the final product, are positive for mutagenesis in the Ames assay. One of these intermediates was also positive in the mouse lymphoma assay. Imatinib was not genotoxic when tested in an in vitro bacterial cell assay (Ames test), an in vitro mammalian cell assay (mouse lymphoma) and an in vivo rat micronucleus assay.

In a study of fertility, male rats were dosed for 70 days prior to mating and female rats were dosed 14 days prior to mating and through to gestational Day 6. Testicular and epididymal weights and percent motile sperm were decreased at 60 mg/kg, approximately three-fourths the maximum clinical dose of 800 mg/day based on BSA. This was not seen at doses less than or equal to 20 mg/kg (one-fourth the maximum human dose of 800 mg). The fertility of male and female rats was not affected.

Fertility was not affected in the preclinical fertility and early embryonic development study although lower testes and epididymal weights as well as a reduced number of motile sperm were observed in the high dose males rats. In the preclinical pre- and postnatal study in rats, fertility in the first generation offspring was also not affected by imatinib mesylate.

13.2 Animal Toxicology and/or Pharmacology

Toxicities from Long-Term Use

It is important to consider potential toxicities suggested by animal studies, specifically, liver, kidney, and cardiac toxicity and immunosuppression. Severe liver toxicity was observed in dogs treated for 2 weeks, with elevated liver enzymes, hepatocellular necrosis, bile duct necrosis, and bile duct hyperplasia. Renal toxicity was observed in monkeys treated for 2 weeks, with focal mineralization and dilation of the renal tubules and tubular nephrosis. Increased blood urea nitrogen (BUN) and creatinine were observed in several of these animals. An increased rate of opportunistic infections was observed with chronic imatinib treatment in laboratory animal studies. In a 39 week monkey study, treatment with imatinib resulted in worsening of normally suppressed malarial infections in these animals. Lymphopenia was observed in animals (as in humans). Additional long-term toxicities were identified in a 2-year rat study. Histopathological examination of the treated rats that died on study revealed cardiomyopathy (both sexes), chronic progressive nephropathy (females) and preputial gland papilloma as principal causes of death or reasons for sacrifice. Non-neoplastic lesions seen in this 2-year study which were not identified in earlier preclinical studies were the cardiovascular system, pancreas, endocrine organs, and teeth. The most important changes included cardiac hypertrophy and dilatation, leading to signs of cardiac insufficiency in some animals.

14 CLINICAL STUDIES

14.1 Chronic Myeloid Leukemia

Chronic Phase, Newly Diagnosed:

An open-label, multicenter, international randomized Phase 3 study (imatinib versus IFN+Ara-C) has been conducted in patients with newly diagnosed Philadelphia chromosome positive (Ph+) chronic myeloid leukemia (CML) in chronic phase. This study compared treatment with either single-agent imatinib or a combination of interferon-alpha (IFN) plus cytarabine (Ara-C). Patients were allowed to cross over to the alternative treatment arm if they failed to show a complete hematologic response (CHR) at 6 months, a major cytogenetic response (MCyR) at 12 months, or if they lost a CHR or MCyR. Patients with increasing WBC or severe intolerance to treatment were also allowed to cross over to the alternative treatment arm with the permission of the study monitoring committee (SMC). In the imatinib arm, patients were treated initially with 400 mg daily. Dose escalations were allowed from 400 mg daily to 600 mg daily, then from 600 mg daily to 800 mg daily. In the IFN arm, patients were treated with a target dose of IFN of 5 MIU/m^2/day subcutaneously in combination with subcutaneous Ara-C 20 mg/m^2/day for 10 days/month.

A total of 1106 patients were randomized from 177 centers in 16 countries, 553 to each arm. Baseline characteristics were well balanced between the two arms. Median age was 51 years (range, 18 to 70 years), with 21.9% of patients greater than or equal to 60 years of age. There were 59% males and 41% females; 89.9% White and 4.7% Black patients. At the cut-off for this analysis (7 years after last patient had been recruited), the median duration of first-line treatment was 82 and 8 months in the imatinib and IFN arm, respectively. The median duration of second-line treatment with imatinib was 64 months. Sixty percent of patients randomized to imatinib are still receiving first-line treatment. In these patients, the average dose of imatinib was 403 mg ± 57 mg. Overall, in patients receiving first line imatinib, the average daily dose delivered was 406 mg ± 76 mg. Due to discontinuations and cross-overs, only 2% of patients randomized to IFN were still on first-line treatment. In the IFN arm, withdrawal of consent (14%) was the most frequent reason for discontinuation of first-line therapy, and the most frequent reason for cross over to the imatinib arm was severe intolerance to treatment (26%) and progression (14%).

The primary efficacy endpoint of the study was progression-free survival (PFS). Progression was defined as any of the following events: progression to accelerated phase or blast crisis (AP/BC), death, loss of CHR or MCyR, or in patients not achieving a CHR an increasing WBC despite appropriate therapeutic management. The protocol specified that the progression analysis would compare the intent to treat (ITT) population: patients randomized to receive imatinib were compared with patients randomized to receive IFN. Patients that crossed over prior to progression were not censored at the time of cross-over, and events that occurred in these patients following cross-over were attributed to the original randomized treatment. The estimated rate of progression-free survival at 84 months in the ITT population was 81.2% [95% CI: 78, 85] in the imatinib arm and 60.6% [56, 65] in the IFN arm (p less than 0.0001, log-rank test), (Figure 1).

With 7 years follow up there were 93 (16.8%) progression events in the imatinib arm: 37 (6.7%) progression to AP/BC, 31 (5.6%) loss of MCyR, 15 (2.7%) loss of CHR or increase in WBC and 10 (1.8%) CML unrelated deaths. In contrast, there were 165 (29.8%) events in the IFN+Ara-C arm of which 130 occurred during first-line treatment with IFN-Ara-C. The estimated rate of patients free of progression to accelerated phase (AP) or blast crisis (BC) at 84 months was 92.5% [90, 95] in the imatinib arm compared to the 85.1%, [82, 89] (p less than or equal to 0.001) in the IFN arm, (Figure 2). The annual rates of any progression events have decreased with time on therapy. The probability of remaining progression free at 60 months was 95% for patients who were in complete cytogenetic response (CCyR) with molecular response (greater than or equal to 3 log reduction in BCR-ABL transcripts as measured by quantitative reverse transcriptase polymerase chain reaction) at 12 months, compared to 89% for patients in CCyR but without a major molecular response and 70% in patients who were not in CCyR at this time point (p less than 0.001).

Figure 1: Progression Free Survival (ITT Principle)

Figure 2: Time to Progression to AP or BC (ITT Principle)

A total of 71 (12.8%) and 85 (15.4%) patients died in the imatinib and IFN+Ara-C group, respectively. At 84 months the estimated overall survival is 86.4% (83, 90) vs 83.3% (80, 87) in the randomized imatinib and the IFN+Ara-C group, respectively (p = 0.073 log-rank test). The hazard ratio is 0.750 with 95% CI 0.547-1.028. This time-to-event endpoint may be affected by the high crossover rate from IFN+Ara-C to imatinib. Major cytogenetic response, hematologic response, evaluation of minimal residual disease (molecular response), time to accelerated phase or blast crisis and survival were main secondary endpoints. Response data are shown in Table 18. Complete hematologic response, major cytogenetic response and CCyR were also statistically significantly higher in the imatinib arm compared to the IFN + Ara- C arm (no cross-over data considered for evaluation of responses). Median time to CCyR in the 454 responders was 6 months (range, 2 to 64 months, 25th to 75th percentiles = 3 to 11 months) with 10% of responses seen only after 22 months of therapy.

Table 18: Response in Newly Diagnosed CML Study (84-Month Data)
 | Imatinib | IFN+Ara-C
Best response rate | n = 553 | n = 553
Hematologic response [Hematologic response criteria (all responses to be confirmed after greater than or equal to 4 weeks): WBC less than 10 x 10^9/L, platelet less than 450 x 10^9/L, myelocyte + metamyelocyte less than 5% in blood, no blasts and promyelocytes in blood, no extramedullary involvement.]
CHR rate n (%) | 534 (96.6%) [p less than 0.001, Fischer's exact test.] | 313 (56.6%)†
[95% CI] | [94.7%, 97.9%] | [52.4%, 60.8%]
Cytogenetic response [Cytogenetic response criteria (confirmed after greater than or equal to 4 weeks): complete (0% Ph+ metaphases) or partial (1%- 35%). A major response (0%-35%) combines both complete and partial responses.]
Major cytogenetic response n (%) | 472 (85.4%)† | 93 (16.8%)†
[95% CI] | [82.1%, 88.2%] | [13.8%, 20.2%]
Unconfirmed [Unconfirmed cytogenetic response is based on a single bone marrow cytogenetic evaluation, therefore unconfirmed complete or partial cytogenetic responses might have had a lesser cytogenetic response on a subsequent bone marrow evaluation.] | 88.6%† | 23.3%†
Complete cytogenetic response n (%) | 413 (74.7%)† | 36 (6.5%)†
[95% CI] | [70.8, 78.3] | [4.6, 8.9]
Unconfirmed§ | 82.5%† | 11.6%†

Molecular response was defined as follows: in the peripheral blood, after 12 months of therapy, reduction of greater than or equal to 3 logarithms in the amount of BCR-ABL transcripts (measured by real-time quantitative reverse transcriptase PCR assay) over a standardized baseline. Molecular response was only evaluated in a subset of patients who had a CCyR by 12 months or later (N = 333). The molecular response rate in patients who had a CCyR in the imatinib arm was 59% at 12 months and 72% at 24 months.

Physical, functional, and treatment-specific biologic response modifier scales from the FACT-BRM (Functional Assessment of Cancer Therapy - Biologic Response Modifier) instrument were used to assess patient-reported general effects of interferon toxicity in 1,067 patients with CML in chronic phase. After one month of therapy to 6 months of therapy, there was a 13% to 21% decrease in median index from baseline in patients treated with IFN, consistent with increased symptoms of IFN toxicity. There was no apparent change from baseline in median index for patients treated with imatinib.

An open-label, multicenter, randomized trial (imatinib versus nilotinib) was conducted to determine the efficacy of imatinib versus nilotinib in adult patients with cytogenetically confirmed, newly diagnosed Ph+ CML-CP. Patients were within 6 months of diagnosis and were previously untreated for CML-CP, except for hydroxyurea and/or anagrelide.

Efficacy was based on a total of 846 patients: 283 patients in the imatinib 400 mg once daily group, 282 patients in the nilotinib 300 mg twice daily group, 281 patients in the nilotinib 400 mg twice daily group.

Median age was 46 years in the imatinib group and 47 years in both nilotinib groups, with 12%, 13%, and 10% of patients greater than or equal to 65 years of age in imatinib 400 mg once daily, nilotinib 300 mg twice daily and nilotinib 400 mg twice daily treatment groups, respectively. There were slightly more male than female patients in all groups (56%, 56%, and 62% in imatinib 400 mg once daily, nilotinib 300 mg twice daily and nilotinib 400 mg twice-daily treatment groups, respectively). More than 60% of all patients were White, and 25% were Asian.

The primary data analysis was performed when all 846 patients completed 12 months of treatment or discontinued earlier. Subsequent analyses were done when patients completed 24, 36, 48, and 60 months of treatment or discontinued earlier. The median time on treatment was approximately 61 months in all three treatment groups.

The primary efficacy endpoint was major molecular response (MMR) at 12 months after the start of study medication. MMR was defined as less than or equal to 0.1% BCR-ABL/ABL % by international scale measured by RQ-PCR, which corresponds to a greater than or equal to 3 log reduction of BCR-ABL transcript from standardized baseline. Efficacy endpoints are summarized in Table 19.

Twelve patients in the imatinib arm progressed to either accelerated phase or blast crises (7 patients within first 6 months, 2 patients within 6 to 12 months, 2 patients within 12 to 18 months and 1 patient within 18 to 24 months) while two patients on the nilotinib arm progressed to either accelerated phase or blast crisis (both within the first 6 months of treatment).

Table 19: Efficacy (MMR and CCyR) of Imatinib Compared to Nilotinib in Newly Diagnosed Ph+ CML-CP
 | Imatinib; 400 mg; once daily | Nilotinib; 300 mg; twice daily
 | N = 283 | N = 282
MMR at 12 months (95% CI) | 22% (17.6, 27.6) | 44% (38.4, 50.3)
P-Value [CMH test stratified by Sokal risk group.] | < 0.0001
CCyR [CCyR: 0% Ph+ metaphases. Cytogenetic responses were based on the percentage of Ph-positive metaphases among greater than or equal to 20 metaphase cells in each bone marrow sample.] by 12 months (95% CI) | 65% (59.2, 70.6) | 80% (75.0, 84.6)
MMR at 24 months (95% CI) | 38% (31.8, 43.4) | 62% (55.8, 67.4)
CCyR† y 24 months (95% CI) | 77% (71.7, 81.8) | 87% (82.4, 90.6)
Abbreviations: CCyR, complete cytogenetic response; MMR, major molecular response; Ph+ CML-CP, Philadelphia chromosome positive chronic myeloid leukemia-chronic phase.

By 60 months, MMR was achieved by 60% of patients on imatinib and 77% of patients on nilotinib.

Median overall survival was not reached in either arm. At the time of the 60-month final analysis, the estimated survival rate was 91.7% for patients on imatinib and 93.7% for patients on nilotinib.

Late Chronic Phase CML and Advanced Stage CML: Three international, open-label, single-arm Phase 2 studies were conducted to determine the safety and efficacy of imatinib in patients with Ph+ CML: 1) in the chronic phase after failure of IFN therapy, 2) in accelerated phase disease, or 3) in myeloid blast crisis. About 45% of patients were women and 6% were Black. In clinical studies, 38% to 40% of patients were greater than or equal to 60 years of age and 10% to 12% of patients were greater than or equal to 70 years of age.

Chronic Phase, Prior Interferon-Alpha Treatment: 532 patients were treated at a starting dose of 400 mg; dose escalation to 600 mg was allowed. The patients were distributed in three main categories according to their response to prior interferon: failure to achieve (within 6 months), or loss of a complete hematologic response (29%), failure to achieve (within 1 year) or loss of a major cytogenetic response (35%), or intolerance to interferon (36%). Patients had received a median of 14 months of prior IFN therapy at doses greater than or equal to 25 x 10^6 units/week and were all in late chronic phase, with a median time from diagnosis of 32 months. Effectiveness was evaluated on the basis of the rate of hematologic response and by bone marrow exams to assess the rate of major cytogenetic response (up to 35% Ph+ metaphases) or CCyR (0% Ph+ metaphases). Median duration of treatment was 29 months with 81% of patients treated for greater than or equal to 24 months (maximum = 31.5 months). Efficacy results are reported in Table 20. Confirmed major cytogenetic response rates were higher in patients with IFN intolerance (66%) and cytogenetic failure (64%), than in patients with hematologic failure (47%). Hematologic response was achieved in 98% of patients with cytogenetic failure, 94% of patients with hematologic failure, and 92% of IFN-intolerant patients.

Accelerated Phase: 235 patients with accelerated phase disease were enrolled. These patients met one or more of the following criteria: greater than or equal to 15% - less than 30% blasts in PB or BM; greater than or equal to 30% blasts + promyelocytes in PB or BM; greater than or equal to 20% basophils in PB; and less than 100 x 10^9/L platelets. The first 77 patients were started at 400 mg, with the remaining 158 patients starting at 600 mg.

Effectiveness was evaluated primarily on the basis of the rate of hematologic response, reported as either complete hematologic response, no evidence of leukemia (i.e., clearance of blasts from the marrow and the blood, but without a full peripheral blood recovery as for complete responses), or return to chronic phase CML. Cytogenetic responses were also evaluated. Median duration of treatment was 18 months with 45% of patients treated for greater than or equal to 24 months (maximum = 35 months). Efficacy results are reported in Table 20. Response rates in accelerated phase CML were higher for the 600 mg dose group than for the 400 mg group: hematologic response (75% vs 64%), confirmed and unconfirmed major cytogenetic response (31% vs 19%).

Myeloid Blast Crisis: 260 patients with myeloid blast crisis were enrolled. These patients had greater than or equal to 30% blasts in PB or BM and/or extramedullary involvement other than spleen or liver; 95 (37%) had received prior chemotherapy for treatment of either accelerated phase or blast crisis (“pretreated patients”) whereas 165 (63%) had not (“untreated patients”). The first 37 patients were started at 400 mg; the remaining 223 patients were started at 600 mg.

Effectiveness was evaluated primarily on the basis of rate of hematologic response, reported as either complete hematologic response, no evidence of leukemia, or return to chronic phase CML using the same criteria as for the study in accelerated phase. Cytogenetic responses were also assessed. Median duration of treatment was 4 months with 21% of patients treated for greater than or equal to 12 months and 10% for greater than or equal to 24 months (maximum = 35 months). Efficacy results are reported in Table 20. The hematologic response rate was higher in untreated patients than in treated patients (36% vs 22%, respectively) and in the group receiving an initial dose of 600 mg rather than 400 mg (33% vs 16%). The confirmed and unconfirmed major cytogenetic response rate was also higher for the 600-mg dose group than for the 400-mg dose group (17% vs 8%).

Table 20: Response in Chronic Myeloid Leukemia Studies
 | Chronic phase IFN failure; (n = 532) | Accelerated phase; (n = 235) | Myeloid blast crisis; (n = 260)
 |  | 600 mg n = 158 | 600 mg n = 223
 | 400 mg | 400 mg n = 77 | 400 mg n = 37
 |  | % of patients [CI 95%]
Hematologic response [Hematologic response criteria (all responses to be confirmed after greater than or equal to 4 weeks): CHR: Chronic phase study [WBC less than 10 x 10^9/L, platelet less than 450 x 10^9/L, myelocytes + metamyelocytes less than 5% in blood, no blasts and promyelocytes in blood, basophils less than 20%, no extramedullary involvement] and in the accelerated and blast crisis studies [absolute neutrophil count (ANC) greater than or equal to 1.5 x 10^9/L, platelets greater than or equal to 100 x 10^9/L, no blood blasts, BM blasts less than 5% and no extramedullary disease]. NEL: Same criteria as for CHR but ANC greater than or equal to 1 x 10^9/L and platelets greater than or equal to 20 x 10^9/L (accelerated and blast crisis studies). RTC: less than 15% blasts BM and PB, less than 30% blasts + promyelocytes in BM and PB, less than 20% basophils in PB, no extramedullary disease other than spleen and liver (accelerated and blast crisis studies).] | 95% [92.3-96.3] | 71% [64.8-76.8] | 31% [25.2-36.8]
Complete hematologic response (CHR) | 95% | 38% | 7%
No evidence of leukemia (NEL) | Not applicable | 13% | 5%
Return to chronic phase (RTC) | Not applicable | 20% | 18%
Major cytogenetic response [Cytogenetic response criteria (confirmed after greater than or equal to 4 weeks): complete (0% Ph+ metaphases) or partial (1%- 35%). A major response (0%-35%) combines both complete and partial responses.] | 60% [55.3-63.8] | 21% [16.2-27.1] | 7% [4.5-11.2]
(Unconfirmed [Unconfirmed cytogenetic response is based on a single bone marrow cytogenetic evaluation, therefore unconfirmed complete or partial cytogenetic responses might have had a lesser cytogenetic response on a subsequent bone marrow evaluation.]) | (65%) | (27%) | (15%)
Complete [Complete cytogenetic response confirmed by a second bone marrow cytogenetic evaluation performed at least 1 month after the initial bone marrow study.] (Unconfirmed‡) | 39% (47%) | 16% (20%) | 2% (7%)
Abbreviations: BM, bone marrow; PB, peripheral blood.

The median time to hematologic response was 1 month. In late chronic phase CML, with a median time from diagnosis of 32 months, an estimated 87.8% of patients who achieved MCyR maintained their response 2 years after achieving their initial response. After 2 years of treatment, an estimated 85.4% of patients were free of progression to AP or BC, and estimated overall survival was 90.8% [88.3, 93.2]. In accelerated phase, median duration of hematologic response was 28.8 months for patients with an initial dose of 600 mg (16.5 months for 400 mg). An estimated 63.8% of patients who achieved MCyR were still in response 2 years after achieving initial response. The median survival was 20.9 [13.1, 34.4] months for the 400 mg group and was not yet reached for the 600 mg group (p = 0.0097). An estimated 46.2% [34.7, 57.7] vs 65.8% [58.4, 73.3] of patients were still alive after 2 years of treatment in the 400 mg vs 600 mg dose groups, respectively. In blast crisis, the estimated median duration of hematologic response is 10 months. An estimated 27.2% [16.8, 37.7] of hematologic responders maintained their response 2 years after achieving their initial response. Median survival was 6.9 [5.8, 8.6] months, and an estimated 18.3% [13.4, 23.3] of all patients with blast crisis were alive 2 years after start of study.

Efficacy results were similar in men and women and in patients younger and older than age 65. Responses were seen in Black patients, but there were too few Black patients to allow a quantitative comparison.

14.2 Pediatric CML

A total of 51 pediatric patients with newly diagnosed and untreated CML in chronic phase were enrolled in an open-label, multicenter, single-arm Phase 2 trial. Patients were treated with imatinib 340 mg/m^2/day, with no interruptions in the absence of dose limiting toxicity. Complete hematologic response (CHR) was observed in 78% of patients after 8 weeks of therapy. The complete cytogenetic response rate (CCyR) was 65%, comparable to the results observed in adults.

Additionally, partial cytogenetic response (PCyR) was observed in 16%. The majority of patients who achieved a CCyR developed the CCyR between Months 3 and 10 with a median time to response based on the Kaplan-Meier estimate of 6.74 months. Patients were allowed to be removed from protocol therapy to undergo alternative therapy, including hematopoietic stem cell transplantation. Thirty-one children received stem cell transplantation. Of the 31 children, 5 were transplanted after disease progression on study and 1 withdrew from study during first week treatment and received transplant approximately 4 months after withdrawal. Twenty-five children withdrew from protocol therapy to undergo stem cell transplant after receiving a median of 9 twenty-eight day courses (range, 4 to 24). Of the 25 patients 13 (52%) had CCyR and 5 (20%) had PCyR at the end of protocol therapy.

One open-label, single-arm study enrolled 14 pediatric patients with Ph+ chronic phase CML recurrent after stem cell transplant or resistant to interferon-alpha therapy. These patients had not previously received imatinib and ranged in age from 3 to 20 years old; 3 were 3 to 11 years old, 9 were 12 to 18 years old, and 2 were greater than 18 years old. Patients were treated at doses of 260 mg/m^2/day (n = 3) (approximately 0.8 times the recommended pediatric dosage of Imkeldi), 340 mg/m^2/day (n = 4), 440 mg/m^2/day (n = 5) (approximately 1.3 times the recommended pediatric dosage of Imkeldi) and 570 mg/m^2/day (n = 2) (approximately 1.7 times the recommended pediatric dosage of Imkeldi). In the 13 patients for whom cytogenetic data are available, 4 achieved a major cytogenetic response, 7 achieved a CCyR, and 2 had a minimal cytogenetic response.

In a second study, 2 of 3 patients with Ph+ chronic phase CML resistant to interferon-alpha therapy achieved a CCyR at doses of 242 mg/m^2/day and 257 mg/m^2/day (0.7 and 0.8 times the recommended pediatric dosage of Imkeldi, respectively).

14.3 Acute Lymphoblastic Leukemia

A total of 48 Philadelphia chromosome positive acute lymphoblastic leukemia (Ph+ ALL) patients with relapsed/refractory disease were studied, 43 of whom received the recommended imatinib dose of 600 mg/day. In addition 2 patients with relapsed/refractory Ph+ ALL received imatinib 600 mg/day in a Phase 1 study.

Confirmed and unconfirmed hematologic and cytogenetic response rates for the 43 relapsed/refractory Ph+ ALL Phase 2 study patients and for the 2 Phase 1 patients are shown in Table 21. The median duration of hematologic response was 3.4 months and the median duration of MCyR was 2.3 months.

Table 21: Effect of Imatinib on Relapsed/Refractory Ph+ ALL
 | Phase 2 study (N = 43) n (%) | Phase 1 study (N = 2) n (%)
CHR | 8 (19) | 2 (100)
NEL | 5 (12)
RTC/PHR | 11 (26)
MCyR | 15 (35)
CCyR | 9 (21)
PCyR | 6 (14)

Abbreviations: CCyR, complete cytogenetic response; CHR, complete hematologic response; MCyR, major cytogenetic response; NEL, no evidence of leukemia; PCyR, partial cytogenic response; Ph+ ALL, Philadelphia chromosome positive acute lymphoblastic leukemia; PHR, partial hematologic response; RTC, return to chronic phase.

14.4 Pediatric ALL

Pediatric and young adult patients with very high risk ALL, defined as those with an expected 5-year event-free survival (EFS) less than 45%, were enrolled after induction therapy on a multicenter, non-randomized cooperative group pilot protocol.

The safety and effectiveness of imatinib (340 mg/m^2/day) in combination with intensive chemotherapy was evaluated in a subgroup of patients with Ph+ ALL. The protocol included intensive chemotherapy and hematopoietic stem cell transplant after 2 courses of chemotherapy for patients with an appropriate HLA-matched family donor. There were 92 eligible patients with Ph+ ALL enrolled. The median age was 9.5 years (1 to 21 years: 2.2% between 1 and less than 2 years, 56.5% between 2 and less than 12 years, 34.8% between 12 and less than 18 years, and 6.5% between 18 and 21 years). Sixty-four percent were male, 75% were White, 9% were Asian/Pacific Islander, and 5% were Black. In 5 successive cohorts of patients, imatinib exposure was systematically increased by earlier introduction and prolonged duration. Cohort 1 received the lowest intensity and cohort 5 received the highest intensity of imatinib exposure.

There were 50 patients with Ph+ ALL assigned to cohort 5 all of whom received imatinib plus chemotherapy; 30 were treated exclusively with chemotherapy and imatinib and 20 received chemotherapy plus imatinib and then underwent hematopoietic stem cell transplant, followed by further imatinib treatment. Patients in cohort 5 treated with chemotherapy received continuous daily exposure to imatinib beginning in the first course of post induction chemotherapy continuing through maintenance cycles 1 through 4 chemotherapy. During maintenance cycles 5 through 12, imatinib was administered 28 days out of the 56 day cycle. Patients who underwent hematopoietic stem cell transplant received 42 days of imatinib prior to HSCT, and 28 weeks (196 days) of imatinib after the immediate post transplant period. The estimated 4-year EFS of patients in cohort 5 was 70% (95% CI: 54, 81). The median follow-up time for EFS at data cutoff in cohort 5 was 40.5 months.

14.5 Myelodysplastic/Myeloproliferative Diseases

An open-label, multicenter, Phase 2 clinical trial was conducted testing imatinib in diverse populations of patients suffering from life-threatening diseases associated with Abl, Kit or PDGFR protein tyrosine kinases. This study included 7 patients with MDS/MPD. These patients were treated with imatinib 400 mg daily. The ages of the enrolled patients ranged from 20 to 86 years. A further 24 patients with MDS/MPD aged 2 to 79 years were reported in 12 published case reports and a clinical study. These patients also received imatinib at a dose of 400 mg daily with the exception of three patients who received lower doses. Of the total population of 31 patients treated for MDS/MPD, 14 (45%) achieved a complete hematological response and 12 (39%) a major cytogenetic response (including 10 with a CCyR). Sixteen patients had a translocation, involving chromosome 5q33 or 4q12, resulting in a PDGFR gene re-arrangement. All of these patients responded hematologically (13 completely). Cytogenetic response was evaluated in 12 out of 14 patients, all of whom responded (10 patients completely). Only 1 (7%) out of the 14 patients without a translocation associated with PDGFR gene re-arrangement achieved a complete hematological response and none achieved a major cytogenetic response. A further patient with a PDGFR gene re-arrangement in molecular relapse after bone marrow transplant responded molecularly. Median duration of therapy was 12.9 months (0.8 to 26.7) in the 7 patients treated within the Phase 2 study and ranged between 1 week and more than 18 months in responding patients in the published literature.

Results are provided in Table 22. Response durations of Phase 2 study patients ranged from 141+ days to 457+ days.

Table 22: Response in MDS/MPD
 | Number of patients | Complete hematologic response | Major cytogenetic response
 | N | N (%) | N (%)
Overall population | 31 | 14 (45) | 12 (39)
Chromosome 5 translocation | 14 | 11 (79) | 11 (79)
Chromosome 4 translocation | 2 | 2 (100) | 1 (50)
Others/no translocation | 14 | 1 (7) | 0
Molecular relapse | 1 | NE | NE

Abbreviations: NE, not evaluable; MDS/MPD, myelodysplastic/myeloproliferative disease.

14.6 Aggressive Systemic Mastocytosis

One open-label, multicenter, Phase 2 study was conducted testing imatinib in diverse populations of patients with life- threatening diseases associated with Abl, Kit or PDGFR protein tyrosine kinases. This study included 5 patients with ASM treated with 100 mg to 400 mg of imatinib daily. These 5 patients ranged from 49 to 74 years of age. In addition to these 5 patients, 10 published case reports and case series describe the use of imatinib in 23 additional patients with ASM aged 26 to 85 years who also received 100 mg to 400 mg of imatinib daily.

Cytogenetic abnormalities were evaluated in 20 of the 28 ASM patients treated with imatinib from the published reports and in the Phase 2 study. Seven of these 20 patients had the FIP1L1-PDGFRα fusion kinase (or CHIC2 deletion). Patients with this cytogenetic abnormality were predominantly males and had eosinophilia associated with their systemic mast cell disease. Two patients had a Kit mutation in the juxtamembrane region (one Phe522Cys and one K509I) and four patients had a D816V c-Kit mutation (not considered sensitive to imatinib), one with concomitant CML.

Of the 28 patients treated for ASM, 8 (29%) achieved a complete hematologic response and 9 (32%) a partial hematologic response (PHR) (61% overall response rate). Median duration of imatinib therapy for the 5 ASM patients in the Phase 2 study was 13 months (range, 1.4 to 22.3 months) and between 1 month and more than 30 months in the responding patients described in the published medical literature. A summary of the response rates to imatinib in ASM is provided in Table 23. Response durations of literature patients ranged from 1+ to 30+ months.

Table 23: Response in ASM
Cytogenetic abnormality | Number of patients | Complete hematologic response | Partial hematologic response
 | N | N (%) | N (%)
FIP1L1-PDGFRα fusion kinase (or CHIC2 deletion) | 7 | 7 (100) | 0
Juxtamembrane mutation | 2 | 0 | 2 (100)
Unknown or no cytogenetic abnormality detected | 15 | 0 | 7 (44)
D816V mutation | 4 | 1 [Patient had concomitant chronic myeloid leukemia CML and ASM.] (25) | 0
Total | 28 | 8 (29) | 9 (32)
Abbreviations: ASM, aggressive systemic mastocytosis; PDGFR, platelet-derived growth factor receptor.

Imatinib has not been shown to be effective in patients with less aggressive forms of systemic mastocytosis (SM). Imkeldi is therefore not recommended for use in patients with cutaneous mastocytosis, indolent systemic mastocytosis (smoldering SM or isolated bone marrow mastocytosis), SM with an associated clonal hematological non-mast cell lineage disease, mast cell leukemia, mast cell sarcoma or extracutaneous mastocytoma. Patients that harbor the D816V mutation of c-Kit are not sensitive to imatinib and should not receive imatinib.

14.7 Hypereosinophilic Syndrome/Chronic Eosinophilic Leukemia

One open-label, multicenter, Phase 2 study was conducted testing imatinib in diverse populations of patients with life- threatening diseases associated with Abl, Kit or PDGFR protein tyrosine kinases. This study included 14 patients with Hypereosinophilic Syndrome/Chronic Eosinophilic Leukemia (HES/CEL). HES patients were treated with 100 mg to 1,000 mg (2.5 times the recommended dosage of Imkeldi) of imatinib daily. The ages of these patients ranged from 16 to 64 years. A further 162 patients with HES/CEL aged 11 to 78 years were reported in 35 published case reports and case series. These patients received imatinib at doses of 75 mg to 800 mg daily. Hematologic response rates are summarized in Table 24. Response durations for literature patients ranged from 6+ weeks to 44 months.

Table 24: Response in HES/CEL
Cytogenetic abnormality | Number of patients | Complete hematological response | Partial hematological response
 |  | N (%) | N (%)
Positive FIP1L1-PDGFRα fusion kinase | 61 | 61 (100) | 0
Negative FIP1L1-PDGFRα fusion kinase | 56 | 12 (21) | 9 (16)
Unknown cytogenetic abnormality | 59 | 34 (58) | 7 (12)
Total | 176 | 107 (61) | 23 (13)

Abbreviations: CEL, chronic eosinophilic leukemia; HES, hypereosinophilic syndrome; PDGFR, platelet-derived growth factor receptor.

14.8 Dermatofibrosarcoma Protuberans

Dermatofibrosarcoma Protuberans (DFSP) is a cutaneous soft tissue sarcoma. It is characterized by a translocation of chromosomes 17 and 22 that results in the fusion of the collagen type 1 alpha 1 gene and the PDGF B gene.

An open-label, multicenter, Phase 2 study was conducted testing imatinib in a diverse population of patients with life- threatening diseases associated with Abl, Kit or PDGFR protein tyrosine kinases. This study included 12 patients with DFSP who were treated with imatinib 800 mg daily (age range, 23 to 75 years). DFSP was metastatic, locally recurrent following initial surgical resection and not considered amenable to further surgery at the time of study entry. A further 6 DFSP patients treated with imatinib are reported in 5 published case reports, their ages ranging from 18 months to 49 years. The total population treated for DFSP therefore comprises 18 patients, 8 of them with metastatic disease. The adult patients reported in the published literature were treated with either 400 mg (4 cases) or 800 mg (1 case) imatinib daily. A single pediatric patient received 400 mg/m2/daily, subsequently increased to 520 mg/m2/daily. Ten patients had the PDGF B gene rearrangement, 5 had no available cytogenetics and 3 had complex cytogenetic abnormalities. Responses to treatment are described in Table 25.

Table 25: Response in DFSP
 | Number of patients (n = 18) | %
Complete response | 7 | 39
Partial response [5 patients made disease free by surgery.] | 8 | 44
Total responders | 15 | 83

Twelve of these 18 patients either achieved a complete response (7 patients) or were made disease free by surgery after a partial response (5 patients, including one child) for a total complete response rate of 67%. A further 3 patients achieved a partial response, for an overall response rate of 83%. Of the 8 patients with metastatic disease, five responded (62%), three of them completely (37%). For the 10 study patients with the PDGF B gene rearrangement, there were 4 complete and 6 partial responses. The median duration of response in the Phase 2 study was 6.2 months, with a maximum duration of 24.3 months, while in the published literature it ranged between 4 weeks and more than 20 months.

14.9 Gastrointestinal Stromal Tumors

Unresectable and/or Malignant Metastatic GIST

Two open-label, randomized, multinational Phase 3 studies were conducted in patients with unresectable or metastatic malignant GIST. The two study designs were similar allowing a predefined combined analysis of safety and efficacy. A total of 1640 patients were enrolled into the two studies and randomized 1:1 to receive either 400 mg or 800 mg orally daily continuously until disease progression or unacceptable toxicity. Patients in the 400 mg daily treatment group who experienced disease progression were permitted to crossover to receive treatment with 800 mg daily. The studies were designed to compare response rates, progression-free survival and overall survival between the dose groups. Median age at patient entry was 60 years. Males comprised 58% of the patients enrolled. All patients had a pathologic diagnosis of CD117 positive unresectable and/or metastatic malignant GIST.

The primary objective of the two studies was to evaluate either progression-free survival (PFS) with a secondary objective of overall survival (OS) in one study or overall survival with a secondary objective of PFS in the other study. A planned analysis of both OS and PFS from the combined datasets from these two studies was conducted. Results from this combined analysis are shown in Table 26.

Table 26: Overall Survival, Progression-Free Survival and Tumor Response Rates in the Phase 3 GIST Trials
 | Imatinib 400 mg | Imatinib 800 mg
 | N = 818 | N = 822
Progression-free survival (months)
Median | 18.9 | 23.2
95% CI | 17.4–21.2 | 20.8–24.9
Overall survival (months) | 49.0 | 48.7
95% CI | 45.3–60.0 | 45.3–51.6
Best overall tumor response
Complete response | 43 (5.3%) | 41 (5.0%)
Partial response | 377 (46.1%) | 402 (48.9%)

Abbreviation: GIST, gastrointestinal stromal tumors.

Median follow up for the combined studies was 37.5 months. There were no observed differences in overall survival between the treatment groups (p = 0.98). Patients who crossed over following disease progression from the 400 mg/day treatment group to the 800 mg/day treatment group (n = 347) had a 3.4 month median and a 7.7 month mean exposure to imatinib following crossover.

One open-label, multinational Phase 2 study was conducted in patients with Kit (CD117) positive unresectable or metastatic malignant GIST. In this study, 147 patients were enrolled and randomized to receive either 400 mg or 600 mg orally every day for up to 36 months. The primary outcome of the study was objective response rate. Tumors were required to be measurable at entry in at least one site of disease, and response characterization was based on Southwestern Oncology Group (SWOG) criteria. There were no differences in response rates between the 2 dose groups. The response rate was 68.5% for the 400 mg group and 67.6% for the 600 mg group. The median time to response was 12 weeks (range was 3 to 98 weeks) and the estimated median duration of response is 118 weeks (95% CI: 86, not reached).

Adjuvant Treatment of GIST

In the adjuvant setting, imatinib was investigated in a multicenter, double-blind, placebo-controlled, randomized trial involving 713 patients (Study 1). Patients were randomized one to one to imatinib at 400 mg/day or matching placebo for 12 months. The ages of these patients ranged from 18 to 91 years. Patients were included who had a histologic diagnosis of primary GIST, expressing KIT protein by immunochemistry and a tumor size greater than or equal to 3 cm in maximum dimension with complete gross resection of primary GIST within 14 to 70 days prior to registration.

Recurrence-free survival (RFS) was defined as the time from date of randomization to the date of recurrence or death from any cause. In a planned interim analysis, the median follow up was 15 months in patients without a RFS event; there were 30 RFS events in the 12-month imatinib arm compared to 70 RFS events in the placebo arm with a hazard ratio of 0.398 (95% CI: 0.259, 0.610), p less than 0.0001. After the interim analysis of RFS, 79 of the 354 patients initially randomized to the placebo arm were eligible to cross over to the 12-month imatinib arm. Seventy-two of these 79 patients subsequently crossed over to imatinib therapy. In an updated analysis, the median follow-up for patients without a RFS event was 50 months. There were 74 (21%) RFS events in the 12-month imatinib arm compared to 98 (28%) events in the placebo arm with a hazard ratio of 0.718 (95% CI: 0.531-0.971) (Figure 3). The median follow-up for OS in patients still living was 61 months. There were 26 (7%) and 33 (9%) deaths in the 12-month imatinib and placebo arms, respectively with a hazard ratio of 0.816 (95% CI: 0.488-1.365).

Figure 3: Study 1 Recurrence-Free Survival (ITT Population)

A second randomized, multicenter, open-label, Phase 3 trial in the adjuvant setting (Study 2) compared 12 months of imatinib treatment to 36 months of imatinib treatment at 400 mg/day in adult patients with KIT (CD117) positive GIST after surgical resection with one of the following: tumor diameter greater than 5 cm and mitotic count greater than 5/50 high power fields (HPF), or tumor diameter greater than 10 cm and any mitotic count, or tumor of any size with mitotic count greater than 10/50 HPF, or tumors ruptured into the peritoneal cavity. There were a total of 397 patients randomized in the trial with 199 patients on the 12-month treatment arm and 198 patients on the 36-month treatment arm. The median age was 61 years (range, 22 to 84 years).

RFS was defined as the time from date of randomization to the date of recurrence or death from any cause. The median follow-up for patients without a RFS event was 42 months. There were 84 (42%) RFS events in the 12-month treatment arm and 50 (25%) RFS events in the 36-month treatment arm. Thirty-six months of imatinib treatment significantly prolonged RFS compared to 12 months of imatinib treatment with a hazard ratio of 0.46 (95% CI: 0.32, 0.65), p less than 0.0001 (Figure 4).

The median follow-up for overall survival (OS) in patients still living was 48 months. There were 25 (13%) deaths in the 12-month treatment arm and 12 (6%) deaths in the 36-month treatment arm. Thirty-six months of imatinib treatment significantly prolonged OS compared to 12 months of imatinib treatment with a hazard ratio of 0.45 (95% CI: 0.22, 0.89), p = 0.0187 (Figure 5).

Figure 4: Study 2 Recurrence-Free Survival (ITT Population)

Figure 5: Study 2 Overall Survival (ITT Population)

15 REFERENCES

1. OSHA Hazardous Drugs. OSHA. [Accessed from http://www.osha.gov/SLTC/hazardousdrugs/index.html]

16 HOW SUPPLIED/STORAGE AND HANDLING

How Supplied

Imkeldi oral solution 80 mg/mL is supplied as 140 mL of clear yellow to brownish yellow colored solution with a strawberry flavor in an amber PET bottle with a child resistant tamper-evident closure.

NDC 81927-201-01

Storage and Handling

Store at 20°C to 25°C (68°F to 77°F); excursions permitted between 15°C and 30°C (59°F and 86°F) [see USP Controlled Room Temperature]. Store and dispense in original container only. Any open bottle should be discarded after 30 days.

Imkeldi is a hazardous drug. Follow applicable special handling and disposal procedures^1.

17 PATIENT COUNSELING INFORMATION

Advise the patient to read the FDA-approved patient labeling (Instructions for Use).

Fluid Retention and Edema

Inform patients of the possibility of developing edema and fluid retention. Advise patients to contact their health care provider if unexpected rapid weight gain occurs [see Warnings and Precautions (5.1)].

Hepatotoxicity

Inform patients of the possibility of developing liver function abnormalities and serious hepatic toxicity. Advise patients to immediately contact their health care provider if signs of liver failure occur, including jaundice, anorexia, bleeding, or bruising [see Warnings and Precautions (5.4)].

Embryo-Fetal Toxicity

Advise pregnant women and females of reproductive potential of the potential risk to a fetus. Advise females of reproductive potential to inform their healthcare provider if they are pregnant or become pregnant [see Warnings and Precautions (5.10) and Use in Specific Populations (8.1)]. Advise females of reproductive potential to use effective contraception during treatment with Imkeldi and for 14 days after the last dose [see Use in Specific Populations (8.3)].

Lactation

Advise women not to breastfeed during treatment with Imkeldi and for 1 month after the last dose [see Use in Specific Populations (8.2)].

Drug Interactions

Imkeldi and certain other medicines, such as warfarin, erythromycin, and phenytoin, including over-the-counter medications, such as herbal products, can interact with each other. Advise patients to tell their doctor if they are taking or plan to take iron supplements. Avoid grapefruit juice and other foods known to inhibit CYP3A4 while taking Imkeldi [see Drug Interactions (7)].

Pediatric

Advise patients that growth retardation has been reported in children and pre-adolescents receiving imatinib. The long term effects of prolonged treatment with Imkeldi on growth in children are unknown. Therefore, closely monitor growth in children under Imkeldi treatment [see Warnings and Precautions (5.11)].

Driving and Using Machines

Advise patients that they may experience side effects, such as dizziness, blurred vision, or somnolence during treatment with Imkeldi. Therefore, caution patients about driving a car or operating machinery [see Warnings and Precautions (5.13)].

Accurate Measuring Device and Dosing and Administration

Advise patients and caregivers to measure Imkeldi with an accurate milliliter measuring device. A household teaspoon is not an accurate measuring device. Advise patients and caregivers to ask their pharmacist to recommend an appropriate press-in bottle adapter and oral dispensing syringe and for instructions for measuring the correct dose [see Warnings and Precautions (5.15)].

Advise patients to take Imkeldi with a meal and a large glass of water. Advise patients that, if a dose is missed, they should wait until the next scheduled dose and not take two doses at the same time. Advise patients to take Imkeldi exactly as prescribed, not to change their dose or to stop taking Imkeldi unless they are told to do so by their doctor [see Dosage and Administration (2.1)].

Manufactured for:

Shorla Oncology Inc.

Cambridge, MA 02142, USA

Patent Information: U.S. Patent: 11,957,681

Version: IMAPI007

INSTRUCTIONS FOR USE

IMKELDI (IM-KELL-DEE)

(imatinib) oral solution

80 mg/mL

This Instructions for Use contains information on how to take (or give) IMKELDI.

Read this Instructions for Use before you (or your child) start using IMKELDI oral solution and each time you get a refill. There may be new information. This important information does not take the place of talking to your (or your child’s) healthcare provider about your (or your child’s) medical condition or treatment.

Supplies needed (Figure A)

IMKELDI bottle with child resistant cap

Oral dispensing syringe (not included with IMKELDI)

Bottle adapter (not included with IMKELDI)

Disposable gloves (not included with IMKELDI)

Figure A

Important Information You Need to Know Before Taking IMKELDI

For oral use only (taken by mouth).

Always use the oral dispensing syringe and bottle adapter provided by your pharmacist. If you did not receive the oral dispensing syringe and bottle adapter, contact your pharmacist.

Ask your pharmacist to show you how to measure your prescribed doses.

Take IMKELDI exactly as prescribed by your healthcare provider. Do not stop taking IMKELDI without first speaking with your healthcare provider.

All doses of IMKELDI should be taken with a meal and a large glass of water. Taking IMKELDI with certain medicines and grapefruit juice may affect each other. Talk to your healthcare provider about all the medicines you take.

If you miss a dose of IMKELDI, do not take the missed dose. Take your next dose at your regular time.

IMKELDI is a hazardous drug. Do not prepare, withdraw, take, or give IMKELDI without wearing disposable gloves.

IMKELDI may cause dizziness, blurred vision, or sleepiness during treatment.

Preparing a new bottle of IMKELDI before first time use

1. Wash hands thoroughly with soap and water (Figure B).

Figure B

2. Wear disposable gloves while preparing, withdrawing, taking, or giving IMKELDI to avoid direct contact with the medicine.

3. Check the expiration date on the bottle. Do not use IMKELDI if the expiration date on the bottle has passed. Contact your healthcare provider or pharmacist.

4. Remove the child-resistant bottle cap by pushing it down firmly and twisting it counter-clockwise (to the left) (Figure C). Do not throw away the child-resistant bottle cap.

Figure C

5. Place the open bottle upright on a clean flat surface. Hold the bottle firmly and push the ribbed end of the bottle adapter firmly into the neck of the bottle as far as it will go (Figure D). Do not remove the bottle adapter from the bottle after it is inserted.

Figure D

6. Put the child-resistant cap back on the bottle by turning it clockwise (to the right) (Figure E). Make sure that the child-resistant cap is tightly closed.

Figure E

7. Write the date of first opening on the bottle label.

Preparing and withdrawing a dose of IMKELDI

8. Repeat Step 1 to Step 4 above.

9. Place the IMKELDI bottle on a clean flat surface.

10. Check your prescription to find out the number of mL you are supposed to take. Find the number line on the oral dispensing syringe barrel that matches your dose.

11. Push the plunger of the oral dispensing syringe all the way up towards the tip of the oral dispensing syringe to remove air (Figure F).

Figure F

12. While keeping the bottle in an upright position, insert the tip of the oral dispensing syringe into the opening of the bottle adapter and push down gently (Figure G).

Do not force the oral dispensing syringe tip into the bottler adapter opening.

Figure G

13. Hold the oral dispensing syringe tip firmly in the bottle and carefully turn the bottle upside down (Figure H). Slowly pull down the plunger of the oral dispensing syringe until the widest part of the oral dispensing syringe plunger lines up with the prescribed number of mL dose (Figure I).

Figure H

Figure I

14. Leave the oral dispensing syringe tip in the bottle adapter. Check the oral dispensing syringe for air (Figure J). If you see air bubbles, push the plunger all the way back up to push the air into the bottle (Figure K). Then pull the plunger down again to withdraw the prescribed dose.

Repeat this Step until all the air is gone from the oral dispensing syringe.

Figure J

Figure K

15. Leave the oral dispensing syringe tip in the bottle adapter. Turn the bottle back to an upright position and place the bottle on a clean flat surface (Figure L). Without touching the plunger, hold the oral dispensing syringe by the barrel and gently twist and pull the oral dispensing syringe out of the bottle adapter (Figure M).

Figure L

Figure M

16. Inspect the oral dispensing syringe to make sure that it contains the correct dose as described in Step 13 (Figure N).

Figure N

Taking (or giving) IMKELDI

17. The child or adult should sit up straight or stand before taking IMKELDI.

18. Gently place the oral dispensing syringe tip in the mouth towards the inside of the cheek (Figure O).

Figure O

19. Slowly and gently push the plunger down to gently squirt the medicine into the inside of the cheek until the plunger no longer moves and all the medicine is out of the oral dispensing syringe (Figure P).

Do not push down too hard on the plunger or squirt the medicine to the back of the mouth or throat as this may cause choking. Remove the oral dispensing syringe from the mouth.

Figure P

20. Swallow the medicine completely. Make sure that no medicine is left in the mouth.

21. After swallowing IMKELDI, eat a meal and drink a large glass of water (Figure Q).

Note: If you do not eat a meal and drink a large glass of water right after swallowing IMKELDI, you may get stomach or intestine problems.

Figure Q

22. Close the bottle by screwing the child-resistant cap back on the bottle in a clockwise direction (to the right) with the adapter left in place. Make sure that the cap is tightly closed (Figure R).

Figure R

Cleaning the oral dispensing syringe after use

23. Right after use, wash the oral dispensing syringe thoroughly with water.

Hold the syringe under water and push the plunger in and out of the oral dispensing syringe several times to remove any medicine from the oral dispensing syringe including the tip (Figure S). Remove the plunger from the oral dispensing syringe barrel and wash both the plunger and oral dispensing syringe barrel thoroughly with cold water.

Repeat this Step until the oral dispensing syringe is clean.

Figure S

24. Shake off excess water from the plunger and the oral dispensing syringe barrel. Dry both the oral dispensing syringe and the oral dispensing syringe plunger with a clean paper towel.

25. Make sure that all oral dispensing syringe parts are fully dry before putting the plunger back in the oral dispensing syringe barrel and using it for the next dose.

26. Throw away (dispose of) the gloves after administration of IMKELDI and cleaning the oral dispensing syringe.

27. Wash hands thoroughly with soap and water.

Storing IMKELDI

Store at room temperature between 68°F to 77°F (20°C to 25°C).

IMKELDI comes in a child resistant tamper-evident bottle.

Store and give in original bottle only.

Keep out of the reach of children.

Throwing away (disposing of) IMKELDI

Any opened bottle should be thrown away (discarded) 30 days after first opening.

Talk to your healthcare provider or pharmacist about the best way to throw away any unused IMKELDI.

Follow all special handling and throw away (disposal) procedures provided by your healthcare provider and pharmacist.

Additional Information

Call your healthcare provider about side effects. You can report side effects to FDA at 1-800-FDA-1088 or www.fda.gov/medwatch. You may also report side effects to Shorla Oncology at 844-9-SHORLA

Manufactured for:

Shorla Oncology Inc.

Cambridge, MA 02142, USA

This Instructions for Use has been approved by the U.S. Food and Drug Administration.

Approved 11/2024

Version: IMAIFU002

Principal Display Panel

NDC 81927-201-01

Rx Only

Imkeldi

(imatinib)

Oral Solution

80 mg/mL

For Oral Use Only

140 mL

Label

Carton